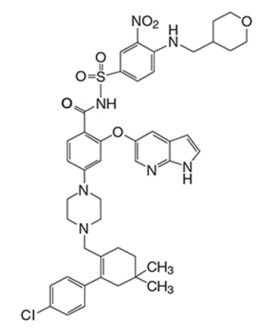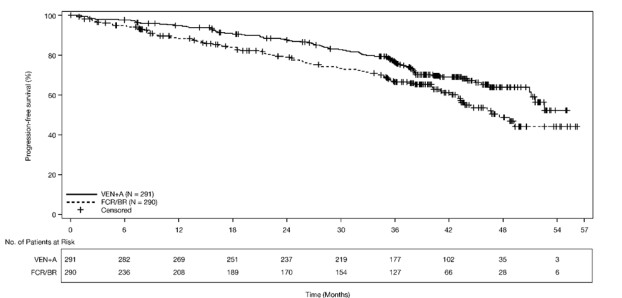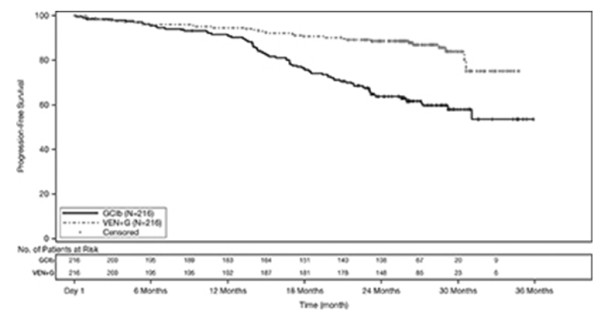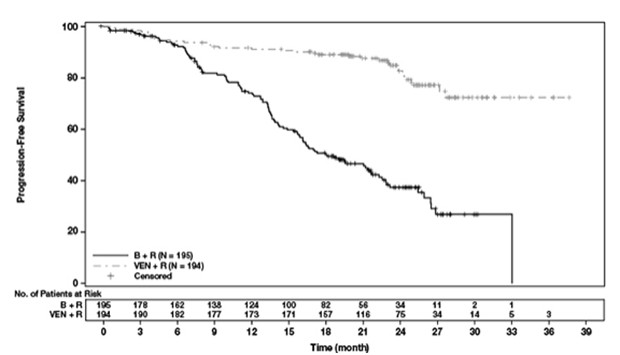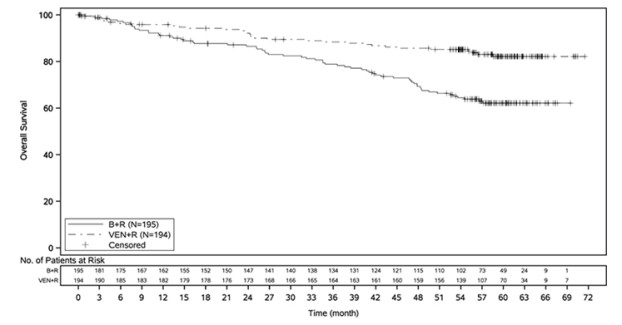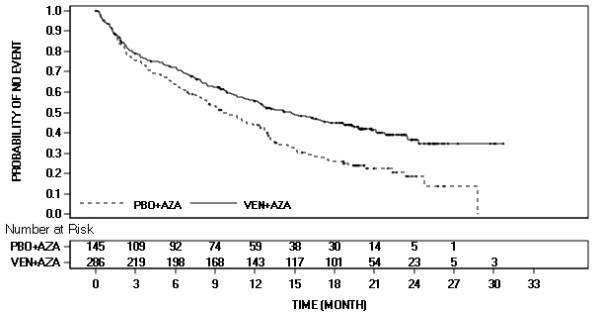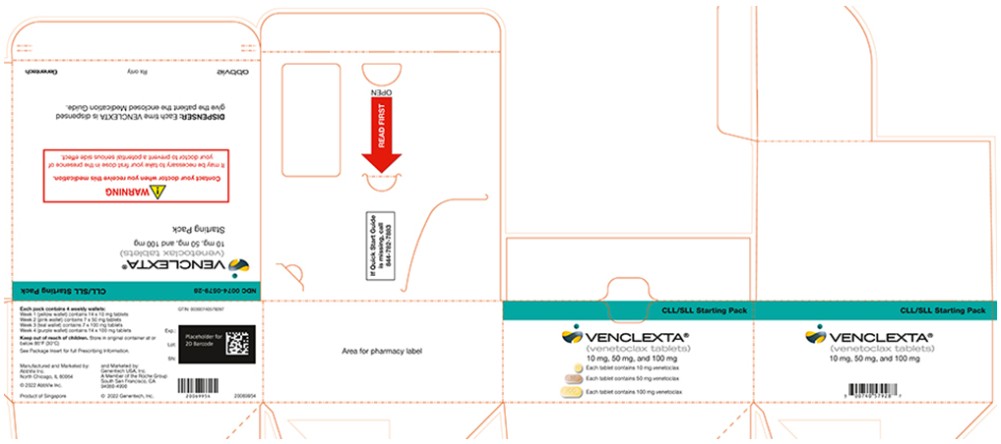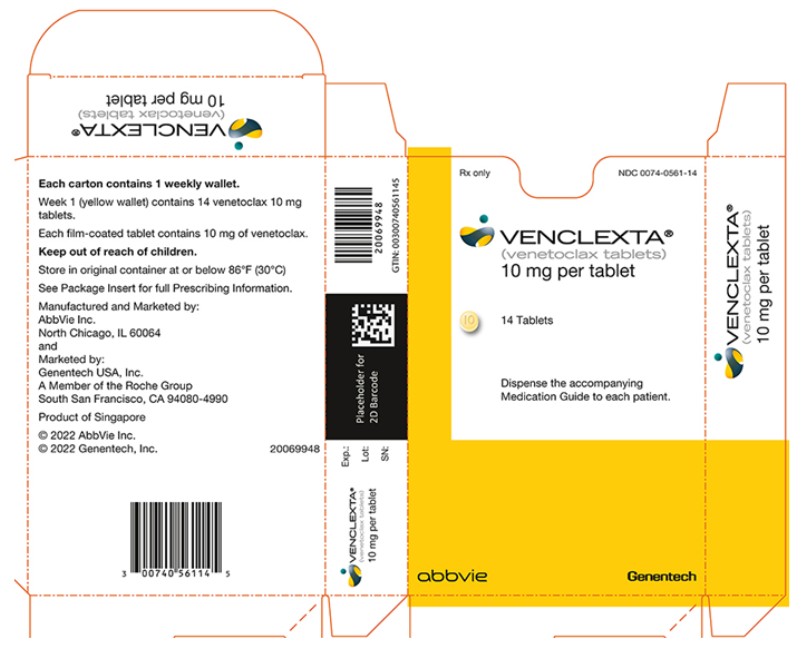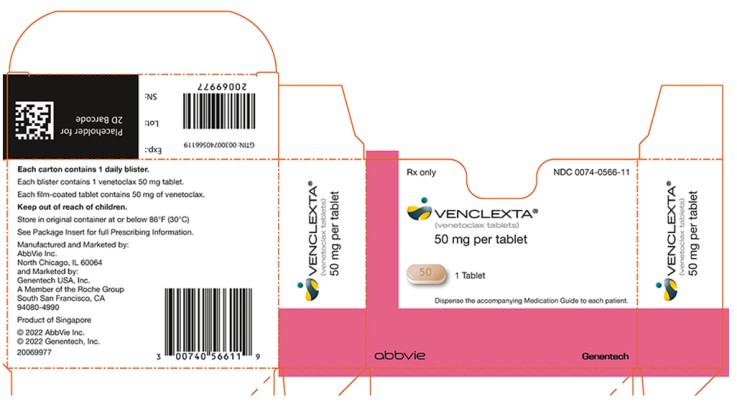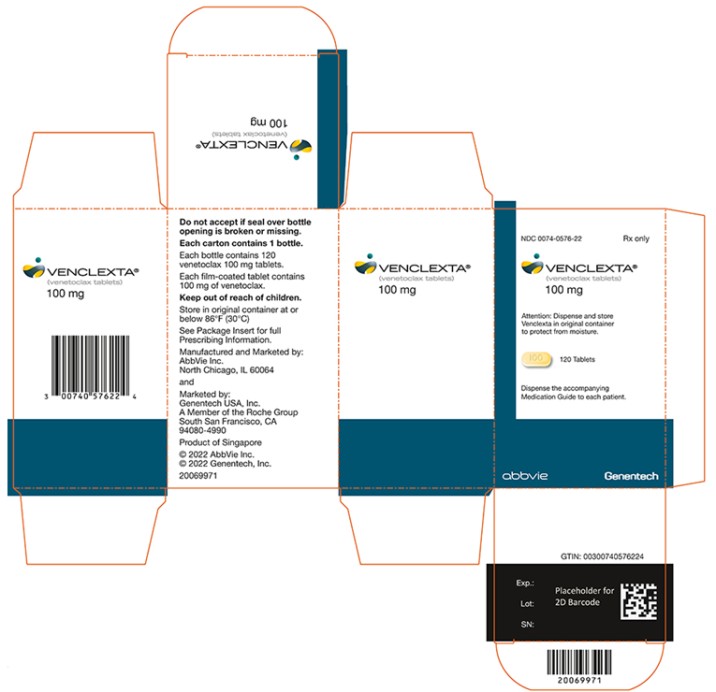 DRUG LABEL: Venclexta
NDC: 0074-0579 | Form: KIT | Route: ORAL
Manufacturer: AbbVie Inc.
Category: prescription | Type: HUMAN PRESCRIPTION DRUG LABEL
Date: 20260219

ACTIVE INGREDIENTS: Venetoclax 10 mg/1 1; Venetoclax 50 mg/1 1; Venetoclax 100 mg/1 1; Venetoclax 100 mg/1 1
INACTIVE INGREDIENTS: COPOVIDONE K25-31; SILICON DIOXIDE; POLYSORBATE 80; SODIUM STEARYL FUMARATE; ANHYDROUS DIBASIC CALCIUM PHOSPHATE; FERRIC OXIDE YELLOW; Talc; TITANIUM DIOXIDE; POLYVINYL ALCOHOL, UNSPECIFIED; POLYETHYLENE GLYCOL, UNSPECIFIED; COPOVIDONE K25-31; SILICON DIOXIDE; POLYSORBATE 80; SODIUM STEARYL FUMARATE; ANHYDROUS DIBASIC CALCIUM PHOSPHATE; FERRIC OXIDE YELLOW; Talc; TITANIUM DIOXIDE; FERRIC OXIDE RED; FERROSOFERRIC OXIDE; POLYVINYL ALCOHOL, UNSPECIFIED; POLYETHYLENE GLYCOL, UNSPECIFIED; COPOVIDONE K25-31; SILICON DIOXIDE; POLYSORBATE 80; SODIUM STEARYL FUMARATE; ANHYDROUS DIBASIC CALCIUM PHOSPHATE; FERRIC OXIDE YELLOW; Talc; TITANIUM DIOXIDE; POLYVINYL ALCOHOL, UNSPECIFIED; POLYETHYLENE GLYCOL, UNSPECIFIED; COPOVIDONE K25-31; SILICON DIOXIDE; POLYSORBATE 80; SODIUM STEARYL FUMARATE; ANHYDROUS DIBASIC CALCIUM PHOSPHATE; FERRIC OXIDE YELLOW; Talc; TITANIUM DIOXIDE; POLYVINYL ALCOHOL, UNSPECIFIED; POLYETHYLENE GLYCOL, UNSPECIFIED

HIGHLIGHTS OF PRESCRIBING INFORMATION

These highlights do not include all the information needed to use VENCLEXTA safely and effectively. See full prescribing information for VENCLEXTA.
VENCLEXTA® (venetoclax tablets), for oral use
Initial U.S. Approval: 2016

RECENT MAJOR CHANGES

Dosage and Administration (2.2, 2.5) | 02/2026
Warnings and Precautions (5.2, 5.3) | 02/2026

1 INDICATIONS AND USAGE

VENCLEXTA is a BCL-2 inhibitor indicated:

- For the treatment of adult patients with chronic lymphocytic leukemia (CLL) or small lymphocytic lymphoma (SLL). (1.1)
- In combination with azacitidine, or decitabine, or low-dose cytarabine for the treatment of newly diagnosed acute myeloid leukemia (AML) in adults 75 years or older, or who have comorbidities that preclude use of intensive induction chemotherapy. (1.2)

2 DOSAGE AND ADMINISTRATION

- See Full Prescribing Information for recommended VENCLEXTA dosages. (2.2, 2.3)
- Take VENCLEXTA tablets orally once daily with a meal and water. Do not chew, crush, or break tablets. (2.8)
- Provide prophylaxis for tumor lysis syndrome. (2.1, 2.4)

3 DOSAGE FORMS AND STRENGTHS

Tablets: 10 mg, 50 mg, 100 mg (3)

4 CONTRAINDICATIONS

Concomitant use with strong CYP3A inhibitors at initiation and during ramp-up phase in patients with CLL/SLL is contraindicated. (2.6, 4, 7.1)

5 WARNINGS AND PRECAUTIONS

- Tumor Lysis Syndrome (TLS): Anticipate TLS; assess risk in all patients. Premedicate with anti-hyperuricemics and ensure adequate hydration. Employ more intensive measures (intravenous hydration, frequent monitoring, hospitalization) as overall risk increases. (2.4, 5.1)
- Neutropenia: Monitor blood counts. Interrupt dosing and resume at same or reduced dose. Consider supportive care measures. (2.5, 5.2)
- Infections: Monitor for signs and symptoms of infection and treat promptly. Withhold for Grade 3 and 4 infection until resolution and resume at same or reduced dose. (2.5, 5.3)
- Immunization: Do not administer live attenuated vaccines prior to, during, or after treatment with VENCLEXTA until B-cell recovery. (5.4)
- Embryo-Fetal Toxicity: May cause embryo-fetal harm. Advise females of reproductive potential of the potential risk to a fetus and to use effective contraception. (5.5)
- Treatment of patients with multiple myeloma with VENCLEXTA in combination with bortezomib plus dexamethasone is not recommended outside of controlled clinical trials. (5.6)

6 ADVERSE REACTIONS

In CLL/SLL, the most common adverse reactions (≥20%) for VENCLEXTA when given in combination with obinutuzumab or rituximab or as monotherapy are neutropenia, thrombocytopenia, anemia, diarrhea, nausea, upper respiratory tract infection, cough, musculoskeletal pain, fatigue, and edema. (6.1) In CLL/SLL, the most common adverse reactions (≥20%) for VENCLEXTA when given in combination with acalabrutinib are neutropenia, headache, diarrhea, musculoskeletal pain, and COVID-19. (6.1)

In AML, the most common adverse reactions (≥30%) in combination with azacitidine or decitabine or low-dose cytarabine are nausea, diarrhea, thrombocytopenia, constipation, neutropenia, febrile neutropenia, fatigue, vomiting, edema, pyrexia, pneumonia, dyspnea, hemorrhage, anemia, rash, abdominal pain, sepsis, musculoskeletal pain, dizziness, cough, oropharyngeal pain, and hypotension. (6.1)

To report SUSPECTED ADVERSE REACTIONS, contact AbbVie Inc. at 1-800-633-9110 or FDA at 1-800-FDA-1088 or www.fda.gov/medwatch.

7 DRUG INTERACTIONS

- Strong or moderate CYP3A inhibitors or P-gp inhibitors: Adjust dosage of VENCLEXTA. (2.6, 7.1)
- Strong or moderate CYP3A inducers: Avoid co-administration. (7.1)
- P-gp substrates: Take at least 6 hours before VENCLEXTA. (7.2)

8 USE IN SPECIFIC POPULATIONS

- Lactation: Advise women not to breastfeed. (8.2)
- Hepatic Impairment: Reduce the VENCLEXTA dose by 50% in patients with severe hepatic impairment. (2.7, 8.7)

FULL PRESCRIBING INFORMATION

1 INDICATIONS AND USAGE

1.1 Chronic Lymphocytic Leukemia/Small Lymphocytic Lymphoma

VENCLEXTA is indicated for the treatment of adult patients with chronic lymphocytic leukemia (CLL) or small lymphocytic lymphoma (SLL).

1.2 Acute Myeloid Leukemia

VENCLEXTA is indicated in combination with azacitidine, or decitabine, or low-dose cytarabine for the treatment of newly diagnosed acute myeloid leukemia (AML) in adults 75 years or older, or who have comorbidities that preclude use of intensive induction chemotherapy.

2 DOSAGE AND ADMINISTRATION

2.1 Important Safety Information

Assess patient-specific factors for level of risk of tumor lysis syndrome (TLS) and provide prophylactic hydration and anti-hyperuricemics to patients prior to first dose of VENCLEXTA to reduce risk of TLS [see Dosage and Administration (2.4) and Warnings and Precautions (5.1)].

2.2 Recommended Dosage for Chronic Lymphocytic Leukemia/Small Lymphocytic Lymphoma

VENCLEXTA dosing begins with a 5-week ramp-up. The 5-week ramp-up dosing schedule is designed to gradually reduce tumor burden (debulk) and decrease the risk of TLS.

VENCLEXTA 5-week Dose Ramp-Up Schedule

Administer VENCLEXTA according to the 5-week ramp-up dosing schedule to the recommended dosage of 400 mg orally once daily as shown in Table 1.

Table 1. Dosing Schedule for 5-Week Ramp-up Phase for Patients with CLL/SLL
 | VENCLEXTA Oral Daily Dose
Week 1 | 20 mg
Week 2 | 50 mg
Week 3 | 100 mg
Week 4 | 200 mg
Week 5 and beyond | 400 mg

The CLL/SLL Starting Pack provides the first 4 weeks of VENCLEXTA according to the ramp-up schedule [see How Supplied/Storage and Handling (16)].

In Combination with Acalabrutinib

Cycle 1 Day 1: Start acalabrutinib 100 mg orally approximately every 12 hours until disease progression, unacceptable toxicity or completion of 14 cycles of treatment. Each cycle is 28 days. Refer to the acalabrutinib prescribing information for additional dosing information.

Cycle 3 Day 1: start VENCLEXTA according to the 5-week ramp-up dosing schedule (see Table 1). After completing the ramp-up phase, continue VENCLEXTA at a dose of 400 mg orally once daily until disease progression, unacceptable toxicity, or until the last day of Cycle 14.

In Combination with Obinutuzumab

Start obinutuzumab administration at 100 mg on Cycle 1 Day 1, followed by 900 mg on Cycle 1 Day 2. Administer 1,000 mg on Days 8 and 15 of Cycle 1 and on Day 1 of each subsequent 28-day cycle for a total of 6 cycles. Refer to the obinutuzumab prescribing information for additional dosing information.

On Cycle 1 Day 22, start VENCLEXTA according to the 5-week ramp-up dosing schedule (see Table 1). After completing the ramp-up phase on Cycle 2 Day 28, continue VENCLEXTA at a dose of 400 mg orally once daily from Cycle 3 Day 1 until the last day of Cycle 12.

In Combination with Rituximab

Start rituximab administration after the patient has completed the 5-week ramp-up dosing schedule for VENCLEXTA (see Table 1) and has received VENCLEXTA at the recommended dosage of 400 mg orally once daily for 7 days. Administer rituximab on Day 1 of each 28-day cycle for 6 cycles, at a dose of 375 mg/m^2 intravenously for Cycle 1 and 500 mg/m^2 intravenously for Cycles 2-6. Continue VENCLEXTA 400 mg orally once daily for 24 months from Cycle 1 Day 1 of rituximab.

Refer to the rituximab prescribing information for additional dosing information.

Monotherapy

The recommended dosage of VENCLEXTA is 400 mg once daily after completion of the 5-week ramp-up dosing schedule (see Table 1). Continue VENCLEXTA until disease progression or unacceptable toxicity.

2.3 Recommended Dosage for Acute Myeloid Leukemia

The recommended dosage and ramp-up of VENCLEXTA depends upon the combination agent. Follow the dosing schedule, including the 3-day or 4-day dose ramp-up, as shown in Table 2. Start VENCLEXTA administration on Cycle 1 Day 1 in combination with:

- Azacitidine 75 mg/m^2 intravenously or subcutaneously once daily on Days 1-7 of each 28-day cycle; OR
- Decitabine 20 mg/m^2 intravenously once daily on Days 1-5 of each 28-day cycle; OR
- Cytarabine 20 mg/m^2 subcutaneously once daily on Days 1-10 of each 28-day cycle.

Table 2. Dosing Schedule for 3- or 4-Day Ramp-up Phase in Patients with AML
 | VENCLEXTA Oral Daily Dose
Day 1 | 100 mg
Day 2 | 200 mg
Day 3 | 400 mg
Days 4 and beyond | 400 mg orally once daily of each 28-day cycle in combination with azacitidine or decitabine | 600 mg orally once daily of each 28-day cycle in combination with low-dose cytarabine

Continue VENCLEXTA, in combination with azacitidine or decitabine or low-dose cytarabine, until disease progression or unacceptable toxicity.

Refer to Clinical Studies (14.2) and Prescribing Information for azacitidine, decitabine, or cytarabine for additional dosing information.

2.4 Risk Assessment and Prophylaxis for Tumor Lysis Syndrome

Patients treated with VENCLEXTA may develop tumor lysis syndrome (TLS). Refer to the appropriate section below for specific details on management. Assess patient-specific factors for level of risk of TLS and provide prophylactic hydration and anti-hyperuricemics to patients prior to first dose of VENCLEXTA to reduce risk of TLS.

Chronic Lymphocytic Leukemia/Small Lymphocytic Lymphoma

VENCLEXTA can cause rapid reduction in tumor and thus poses a risk for TLS in the initial 5-week ramp-up phase. Changes in blood chemistries consistent with TLS that require prompt management can occur as early as 6 to 8 hours following the first dose of VENCLEXTA and at each dose increase. TLS can also occur upon resumption of VENCLEXTA following a dosage interruption. See Table 4, Table 5, and Table 6 for dose modifications of VENCLEXTA after interruption.

The risk of TLS is a continuum based on multiple factors, particularly reduced renal function (creatinine clearance [CLcr] <80 mL/min) and tumor burden; splenomegaly may also increase the risk of TLS.

Perform tumor burden assessments, including radiographic evaluation (e.g., CT scan), assess blood chemistry (potassium, uric acid, phosphorus, calcium, and creatinine) in all patients and correct pre-existing abnormalities prior to initiation of treatment with VENCLEXTA. The risk may decrease as tumor burden decreases [see Warnings and Precautions (5.1) and Use in Specific Populations (8.6)].

Table 3 below describes the recommended TLS prophylaxis and monitoring during VENCLEXTA treatment based on tumor burden determination from clinical trial data. Consider all patient comorbidities before final determination of prophylaxis and monitoring schedule. Reassess the risk of TLS when reinitiating VENCLEXTA after a dosage interruption lasting more than 1 week during the ramp-up phase, or more than 2 weeks after completion of ramp-up. Institute prophylaxis and monitoring as needed.

Table 3. Recommended TLS Prophylaxis Based on Tumor Burden in Patients with CLL/SLL
Tumor Burden |  | Prophylaxis |  | Blood Chemistry Monitoringc,d
 |  | Hydrationa | Anti- hyperuricemicsb | Setting and Frequency of Assessments
Low | All LN <5 cm AND ALC <25 x10^9/L | Oral (1.5 to 2 L) | Allopurinol | Outpatient; - For first dose of 20 mg and 50 mg: Pre-dose, 6 to 8 hours, 24 hours - For subsequent ramp-up doses: Pre-dose
Medium | Any LN 5 to <10 cm OR ALC ≥25 x10^9/L | Oral (1.5 to 2 L) and consider additional intravenous | Allopurinol | Outpatient; - For first dose of 20 mg and 50 mg: Pre-dose, 6 to 8 hours, 24 hours - For subsequent ramp-up doses: Pre-dose - For first dose of 20 mg and 50 mg: Consider hospitalization for patients with CLcr <80ml/min; see below for monitoring in hospital
High | Any LN ≥10 cm OR ALC ≥25 x10^9/L AND any LN ≥5 cm | Oral (1.5 to 2 L) and intravenous (150 to 200 mL/hr as tolerated) | Allopurinol; consider rasburicase if baseline uric acid is elevated | In hospital; - For first dose of 20 mg and 50 mg: Pre-dose, 4, 8, 12, and 24 hours; Outpatient; - For subsequent ramp-up doses: Pre-dose, 6 to 8 hours, 24 hours
ALC = absolute lymphocyte count; CLcr = creatinine clearance; LN = lymph node.
aAdminister intravenous hydration for any patient who cannot tolerate oral hydration.
bStart allopurinol or xanthine oxidase inhibitor 2 to 3 days prior to initiation of VENCLEXTA.
cEvaluate blood chemistries (potassium, uric acid, phosphorus, calcium, and creatinine); review in real time.
dFor patients at risk of TLS, monitor blood chemistries at 6 to 8 hours and at 24 hours at each subsequent ramp-up dose.

Acute Myeloid Leukemia

- All patients should have white blood cell count less than 25 × 10^9/L prior to initiation of VENCLEXTA. Cytoreduction prior to treatment may be required.
- Prior to first VENCLEXTA dose, provide all patients with prophylactic measures including adequate hydration and anti-hyperuricemic agents and continue during ramp-up phase.
- Assess blood chemistry (potassium, uric acid, phosphorus, calcium, and creatinine) and correct pre-existing abnormalities prior to initiation of treatment with VENCLEXTA.
- Monitor blood chemistries for TLS at pre-dose, 6 to 8 hours after each new dose during ramp-up, and 24 hours after reaching final dose.
- For patients with risk factors for TLS (e.g., circulating blasts, high burden of leukemia involvement in bone marrow, elevated pretreatment lactate dehydrogenase [LDH] levels, or reduced renal function), consider additional measures, including increased laboratory monitoring and reducing VENCLEXTA starting dose.

2.5 Dosage Modifications for Adverse Reactions

Chronic Lymphocytic Leukemia/Small Lymphocytic Lymphoma

The recommended dose reductions for VENCLEXTA for adverse reactions are provided in Table 4. The recommended dosage modifications for VENCLEXTA for adverse reactions are provided in Table 5 and Table 6.

For patients having a dosage interruption lasting more than 1 week during the ramp-up phase, or more than 2 weeks after completion of ramp-up, reassess for risk of TLS to determine if reinitiation with a reduced dose is necessary (e.g., all or some levels of the dose ramp-up schedule) [see Dosage and Administration (2.2, 2.4)].

Table 4. Recommended Dose Reduction for Adverse Reactions for VENCLEXTA in CLL/SLL
Dose at Interruption, mg | Restart Dose, mga,b
400 | 300
300 | 200
200 | 100
100 | 50
50 | 20
20 | 10
aDuring the ramp-up phase, continue the reduced dose for 1 week before increasing the dose.
bIf a dosage interruption lasts more than 1 week during the ramp-up phase or more than 2 weeks after completion of ramp-up, reassess the risk of TLS and determine if reinitiation at a reduced dosage is necessary [see Dosage and Administration (2.2, 2.4)].

Table 5. Recommended VENCLEXTA Dosage Modifications for Adverse Reactionsa in Patients with CLL/SLL Receiving VENCLEXTA in Combination with Obinutuzumab, with Rituximab or as Monotherapy

Adverse Reaction | Occurrence | Dosage Modification
Tumor Lysis Syndrome
Blood chemistry changes or symptoms suggestive of TLS [see Warnings and Precautions (5.1)] | Any | Withhold the next day’s dose. If resolved within 24 to 48 hours of last dose, resume at same dose.
 |  | For any blood chemistry changes requiring more than 48 hours to resolve, resume at reduced dose (see Table 4).
 |  | For any events of clinical TLS,b resume at reduced dose following resolution (see Table 4).
Non-Hematologic Adverse Reactions
Grade 3 or 4 non-hematologic toxicities [see Adverse Reactions (6.1)] | 1st occurrence | Interrupt VENCLEXTA. Upon resolution to Grade 1 or baseline level, resume VENCLEXTA at the same dose.
 | 2nd and subsequent occurrences | Interrupt VENCLEXTA. Follow dose reduction guidelines in Table 4 when resuming treatment with VENCLEXTA after resolution. A larger dose reduction may occur at the discretion of the physician.
Hematologic Adverse Reactions
Grade 3 neutropenia with infection or fever; or Grade 4 hematologic toxicities (except lymphopenia) [see Warnings and Precautions (5.2)] | 1st occurrence | Interrupt VENCLEXTA. Upon resolution to Grade 1 or baseline level, resume VENCLEXTA at the same dose.
 | 2nd and subsequent occurrences | Interrupt VENCLEXTA. Follow dose reduction guidelines in Table 4 when resuming treatment with VENCLEXTA after resolution. A larger dose reduction may occur at the discretion of the physician.
Consider discontinuing VENCLEXTA for patients who require dose reductions to less than 100 mg for more than 2 weeks.
aAdverse reactions were graded using NCI CTCAE version 4.0.
bClinical TLS was defined as laboratory TLS with clinical consequences such as acute renal failure, cardiac arrhythmias, or sudden death and/or seizures [see Adverse Reactions (6.1)].

Table 6: Recommended Dosage Modifications for Adverse Reactions in Patients with CLL/SLL Receiving VENCLEXTA in Combination with Acalabrutinib

 | Adverse Reactiona | Adverse Reaction Occurrence | Dose Modification
 | Grade 3 or 4 neutropenia with or without fever and/or infection; Grade 4 neutropenia lasting more than 7 days | First occurrence | Interrupt VENCLEXTA and/or acalabrutinib.b Once toxicity resolves to Grade ≤ 1 or baseline, restart VENCLEXTA and/or acalabrutinib at same dose.
 |  | Second occurrence | Interrupt VENCLEXTA and/or acalabrutinib.b Once toxicity resolves to Grade ≤ 1 or baseline, restart VENCLEXTA at one lower dose level and restart acalabrutinib at same dose.
 |  | Subsequent occurrence | Withhold VENCLEXTA and/or acalabrutinib until toxicity resolves to Grade ≤ 1 or baseline.b,c
 | Grade 3 or 4 thrombocytopenia and/or bleedinge | First occurrence | Interrupt VENCLEXTA and/or acalabrutinib. When bleeding resolves and thrombocytopenia is Grade ≤ 1 or baseline without transfusion support for 5 consecutive days, restart VENCLEXTA and/or acalabrutinib at same dose.
 |  | Second occurrence | Interrupt VENCLEXTA and acalabrutinib until resolution of bleeding and thrombocytopenia resolves to Grade ≤ 1 or baseline. Restart VENCLEXTA at one lower dose level and restart acalabrutinib at same dose.d
 |  | Subsequent occurrences of severe thrombocytopenia | Interrupt VENCLEXTA and acalabrutinib until resolution of bleeding and thrombocytopenia resolves to Grade ≤ 1 or baseline. Restart VENCLEXTA at one lower dose level and resume acalabrutinib at a reduced frequency of 100 mg once daily.c,d
 | Grade 3 or 4 tumour lysis syndrome (TLS) | First and subsequent episodes | If a patient experiences blood chemistry changes suggestive of TLS, the following day’s VENCLEXTA and acalabrutinib dose should be withheld. If resolved within 24–48 hours of last dose, treatment can be resumed at the same dose. For events of clinical TLS or blood chemistry changes requiring more than 48 hours to resolve, resume VENCLEXTA at one lower dose level. When resuming treatment after interruption due to TLS, monitor for TLS and provide prophylaxis.
 | Grade 3 other non-hematologic eventsf | First occurrence | Interrupt VENCLEXTA and/or acalabrutinib until toxicity resolves to Grade ≤ 1. Restart VENCLEXTA and/or acalabrutinib at same dose.
 |  | Second occurrence | Interrupt VENCLEXTA and/or acalabrutinib until toxicity resolves to Grade ≤ 1c.
 | Grade 4 other non-hematologic eventsf | First occurrence | Interrupt VENCLEXTA and/or acalabrutinib until toxicity resolves to Grade ≤ 1. Restart VENCLEXTA at one lower dose level and restart acalabrutinib at a reduced frequency of 100 mg once daily.e
 |  | Second occurrence | Interrupt VENCLEXTA and/or acalabrutinib until toxicity resolves to Grade ≤ 1c.
 | a Adverse reactions graded by the National Cancer Institute Common Terminology Criteria for Adverse Events (NCI CTCAE) version 5.0. b Growth factor may be used at physician discretion. c Clinical judgment of the treating physician should guide the management plan of each patient based on the individual benefit/risk assessment for treatment with VENCLEXTA in combination with acalabrutinib. d Acalabrutinib dose may be re-escalated at the discretion of the physician if patient tolerates a reduced dose for ≥4 weeks. e Platelets may be used at physician discretion. f Certain treatment-emergent non-hematologic AEs (e.g., venous thromboembolic events) may be managed and become clinically stable following medical intervention but may not improve to Grade ≤ 1 according to the NCI CTCAE definitions. In such cases, if a subject is clinically stable, resumption of VENCLEXTA may be possible based on clinical judgement of the treating physician.

Acute Myeloid Leukemia

Monitor blood counts frequently through resolution of cytopenias. Dose modification and interruptions for cytopenias are dependent on remission status. Dose modifications of VENCLEXTA for adverse reactions are provided in Table 7.

Table 7. Recommended VENCLEXTA Dosage Modifications for Adverse Reactions in AML
Adverse Reaction | Occurrence | Dosage Modification
Hematologic Adverse Reactions
Grade 4 neutropenia with or without fever or infection; or Grade 4 thrombocytopenia [see Warnings and Precautions (5.2)] | Occurrence prior to achieving remissiona | In most instances, do not interrupt VENCLEXTA in combination with azacitidine, decitabine, or low-dose cytarabine due to cytopenias prior to achieving remission.
 | First occurrence after achieving remission and lasting at least 7 days | Delay subsequent cycle of VENCLEXTA in combination with azacitidine, decitabine, or low-dose cytarabine and monitor blood counts. Upon resolution to Grade 1 or 2, resume VENCLEXTA at the same dose in combination with azacitidine, decitabine, or low-dose cytarabine.
 | Subsequent occurrences in cycles after achieving remission and lasting 7 days or longer | Delay subsequent cycle of VENCLEXTA in combination with azacitidine, or decitabine, or low-dose cytarabine and monitor blood counts. Upon resolution to Grade 1 or 2, resume VENCLEXTA at the same dose in combination with azacitidine, decitabine, or low-dose cytarabine, and reduce VENCLEXTA duration by 7 days during each of the subsequent cycles, such as 21 days instead of 28 days.
Non-Hematologic Adverse Reactions
Grade 3 or 4 non-hematologic toxicities [see Adverse Reactions (6.1)] | Any occurrence | Interrupt VENCLEXTA if not resolved with supportive care. Upon resolution to Grade 1 or baseline level, resume VENCLEXTA at the same dose.
aRecommend bone marrow evaluation.

2.6 Dosage Modifications for Drug Interactions

Strong or Moderate CYP3A Inhibitors or P-gp Inhibitors

Table 8 describes VENCLEXTA contraindication or dosage modification based on concomitant use with a strong or moderate CYP3A inhibitor or a P-gp inhibitor [see Drug Interactions (7.1)] at initiation, during, or after the ramp-up phase.

Resume the VENCLEXTA dosage that was used prior to concomitant use of a strong or moderate CYP3A inhibitor or a P-gp inhibitor 2 to 3 days after discontinuation of the inhibitor [see Drug Interactions (7.1)].

Table 8. Management of Potential VENCLEXTA Interactions with CYP3A and P-gp Inhibitors
Coadministered Drug | Initiation and Ramp-Up Phase |  | Steady Daily Dose (After Ramp-Up Phase)a
Posaconazole | CLL/SLL | Contraindicated | Reduce VENCLEXTA dose to 70 mg.
 | AML | Day 1 – 10 mg Day 2 – 20 mg Day 3 – 50 mg Day 4 – 70 mg
Other strong CYP3A inhibitor | CLL/SLL | Contraindicated | Reduce VENCLEXTA dose to 100 mg.
 | AML | Day 1 – 10 mg Day 2 – 20 mg Day 3 – 50 mg Day 4 – 100 mg
Moderate CYP3A inhibitor | Reduce the VENCLEXTA dose by at least 50%.
P-gp inhibitor
aIn patients with CLL/SLL, consider alternative medications or reduce the VENCLEXTA dose as described in Table 8.

2.7 Dosage Modifications for Patients with Severe Hepatic Impairment

Reduce the VENCLEXTA once daily dose by 50% for patients with severe hepatic impairment (Child-Pugh C); monitor these patients more closely for adverse reactions [see Use in Specific Populations (8.7)].

2.8 Administration

Instruct patients of the following:

- Take VENCLEXTA with a meal and water.
- Take VENCLEXTA at approximately the same time each day.
- Swallow VENCLEXTA tablets whole. Do not chew, crush, or break tablets prior to swallowing.

The recommended dosage of VENCLEXTA may be delivered using any of the approved tablet strengths (e.g., patients can take 2 x 50 mg tablets or 10 x 10 mg tablets instead of 1 x 100 mg tablet as needed).

If the patient misses a dose of VENCLEXTA within 8 hours of the time it is usually taken, instruct the patient to take the missed dose as soon as possible and resume the normal daily dosing schedule. If a patient misses a dose by more than 8 hours, instruct the patient not to take the missed dose and resume the usual dosing schedule the next day.

If the patient vomits following dosing, instruct the patient to not take an additional dose that day and to take the next prescribed dose at the usual time.

3 DOSAGE FORMS AND STRENGTHS

Table 9. VENCLEXTA Tablet Strength and Description
Tablet Strength | Description of Tablet
10 mg | Round, biconvex shaped, pale yellow film-coated tablet debossed with “V” on one side and “10” on the other side
50 mg | Oblong, biconvex shaped, beige film-coated tablet debossed with “V” on one side and “50” on the other side
100 mg | Oblong, biconvex shaped, pale yellow film-coated tablet debossed with “V” on one side and “100” on the other side

4 CONTRAINDICATIONS

Concomitant use of VENCLEXTA with strong CYP3A inhibitors at initiation and during the ramp-up phase is contraindicated in patients with CLL/SLL due to the potential for increased risk of tumor lysis syndrome [see Dosage and Administration (2.6) and Drug Interactions (7.1)].

5 WARNINGS AND PRECAUTIONS

5.1 Tumor Lysis Syndrome

Tumor lysis syndrome (TLS), including fatal events and renal failure requiring dialysis, has occurred in patients treated with VENCLEXTA [see Adverse Reactions (6.1)].

VENCLEXTA can cause rapid reduction in tumor and thus poses a risk for TLS at initiation and during the ramp-up phase in all patients, and during reinitiation after dosage interruption in patients with CLL/SLL. Changes in blood chemistries consistent with TLS that require prompt management can occur as early as 6 to 8 hours following the first dose of VENCLEXTA and at each dose increase. TLS, including fatal cases, has been reported after a single 20 mg dose of VENCLEXTA.

In patients with CLL/SLL who followed the current (5-week) dose ramp-up and the TLS prophylaxis and monitoring measures, the rate of TLS was 2% in the VENCLEXTA CLL/SLL monotherapy trials. The rate of TLS remained consistent with VENCLEXTA in combination with obinutuzumab or rituximab. With a 2- to 3-week dose ramp-up and higher starting dose in patients with CLL/SLL, the TLS rate was 13% and included deaths and renal failure [see Adverse Reactions (6.1)].

In patients with AML who followed the current 3-day ramp-up dosing schedule and the TLS prophylaxis and monitoring measures, the rate of TLS was 1.1% in patients who received VENCLEXTA in combination with azacitidine (VIALE-A). In patients with AML who followed a 4-day ramp-up dosing schedule and the TLS prophylaxis and monitoring measures, the rate of TLS was 5.6% and included deaths and renal failure in patients who received VENCLEXTA in combination with low-dose cytarabine (VIALE-C) [see Adverse Reactions (6.1)].

The risk of TLS is a continuum based on multiple factors, particularly reduced renal function, tumor burden, and type of malignancy. Splenomegaly may also increase the risk of TLS in patients with CLL/SLL.

Assess all patients for risk and provide appropriate prophylaxis for TLS, including hydration and anti-hyperuricemics. Monitor blood chemistries and manage abnormalities promptly. Employ more intensive measures (intravenous hydration, frequent monitoring, hospitalization) as overall risk increases. Interrupt dosing if needed; when restarting VENCLEXTA, follow dose modification guidance [see Dosage and Administration (2.1, 2.2, 2.3, 2.4) and Use in Specific Populations (8.6)].

Concomitant use of VENCLEXTA with P-gp inhibitors or strong or moderate CYP3A inhibitors increases venetoclax exposure, which may increase the risk of TLS at initiation and during the ramp-up phase of VENCLEXTA. For patients with CLL/SLL, coadministration of VENCLEXTA with strong CYP3A inhibitors at initiation and during the 5-week ramp-up phase is contraindicated [see Contraindications (4)]. For patients with AML, reduce the dose of VENCLEXTA when coadministered with strong CYP3A inhibitors at initiation and during the 3- or 4-day ramp-up phase. For patients with CLL/SLL or AML, reduce the dose of VENCLEXTA when coadministered with moderate CYP3A4 inhibitors or P-gp inhibitors [see Dosage and Administration (2.6) and Drug Interactions (7.1)].

5.2 Neutropenia

In patients with CLL, Grade 3 or 4 neutropenia developed in 63% to 64% of patients and Grade 4 neutropenia developed in 31% to 33% of patients when treated with VENCLEXTA in monotherapy studies and in combination studies with obinutuzumab or rituximab. Febrile neutropenia occurred in 4% to 6% of patients treated with VENCLEXTA in monotherapy studies and in combination studies with obinutuzumab or rituximab [see Adverse Reactions (6.1)].

In patients with CLL, Grade 3 or 4 neutropenia developed in 38% of patients and Grade 4 neutropenia developed in 15% of patients when treated with VENCLEXTA in combination with acalabrutinib. Febrile neutropenia occurred in 2% of patients treated with VENCLEXTA in combination with acalabrutinib [see Adverse Reactions (6.1)].

In patients with AML, baseline neutrophil counts worsened in 95% to 100% of patients treated with VENCLEXTA in combination with azacitidine, decitabine, or low-dose cytarabine. Neutropenia can recur with subsequent cycles.

Monitor complete blood counts throughout the treatment period. For interruption and dose resumption of VENCLEXTA for severe neutropenia, see Table 5 and Table 6 for CLL and Table 7 for AML [see Dosage and Administration (2.5)]. Consider supportive measures, including antimicrobials and growth factors (e.g., G-CSF).

5.3 Infections

Fatal and serious infections, such as pneumonia and sepsis, have occurred in patients treated with VENCLEXTA [see Adverse Reactions (6.1)].

Monitor patients for signs and symptoms of infection and treat promptly. Withhold VENCLEXTA for Grade 3 and 4 infection until resolution. For dose resumptions, see Table 5 and Table 6 for CLL and Table 7 for AML [see Dosage and Administration (2.5)].

In AMPLIFY, a randomized study in patients with previously untreated CLL/SLL, serious or grade 3 or higher infections occurred in 14% of patients who received VENCLEXTA in combination with acalabrutinib (VEN+A), most commonly due to COVID-19.

In an additional cohort of patients receiving VENCLEXTA in combination with acalabrutinib and obinutuzumab (AVO) (an unapproved regimen for previously untreated CLL/SLL in AMPLIFY), serious or Grade 3 or higher infections occurred in 25% receiving AVO compared to 14% in patients receiving VEN+A. Fatal infections occurred in 6% receiving AVO compared to 3.1% of patients receiving VEN+A, most commonly due to COVID-19. The safety and effectiveness of AVO has not been established in patients with previously untreated CLL/SLL [see Clinical Studies (14.1)].

5.4 Immunization

Do not administer live attenuated vaccines prior to, during, or after treatment with VENCLEXTA until B-cell recovery occurs. The safety and efficacy of immunization with live attenuated vaccines during or following VENCLEXTA therapy have not been studied. Advise patients that vaccinations may be less effective.

5.5 Embryo-Fetal Toxicity

Based on findings in animals and its mechanism of action, VENCLEXTA may cause embryo-fetal harm when administered to a pregnant woman. In an embryo-fetal study conducted in mice, administration of venetoclax to pregnant animals at exposures equivalent to that observed in patients at a dose of 400 mg daily resulted in post-implantation loss and decreased fetal weight.

Advise pregnant women of the potential risk to a fetus. Advise females of reproductive potential to use effective contraception during treatment with VENCLEXTA and for 30 days after the last dose [see Use in Specific Populations (8.1, 8.3)].

5.6 Increased Mortality in Patients with Multiple Myeloma when VENCLEXTA is Added to Bortezomib and Dexamethasone

In a randomized trial (BELLINI; NCT02755597) in patients with relapsed or refractory multiple myeloma, the addition of VENCLEXTA to bortezomib plus dexamethasone, a use for which VENCLEXTA is not indicated, resulted in increased mortality. Treatment of patients with multiple myeloma with VENCLEXTA in combination with bortezomib plus dexamethasone is not recommended outside of controlled clinical trials.

6 ADVERSE REACTIONS

The following clinically significant adverse reactions are described elsewhere in the labeling:

- Tumor Lysis Syndrome [see Warnings and Precautions (5.1)]
- Neutropenia [see Warnings and Precautions (5.2)]
- Infections [see Warnings and Precautions (5.3)]

6.1 Clinical Trials Experience

Because clinical trials are conducted under widely variable conditions, adverse event rates observed in clinical trials of a drug cannot be directly compared with rates of clinical trials of another drug and may not reflect the rates observed in practice.

In CLL/SLL, the safety population reflects exposure to VENCLEXTA as monotherapy in patients in M13-982, M14-032, and M12-175 and in combination with obinutuzumab or rituximab in patients in CLL14 and MURANO. In this CLL/SLL safety population, the most common adverse reactions (≥20%) for VENCLEXTA were neutropenia, thrombocytopenia, anemia, diarrhea, nausea, upper respiratory tract infection, cough, musculoskeletal pain, fatigue, and edema.

In the CLL/SLL safety population that reflects exposure to VENCLEXTA in combination with acalabrutinib, the most common adverse reactions (≥20%) were neutropenia, headache, diarrhea, musculoskeletal pain, and COVID-19.

In AML, the safety population reflects exposure to VENCLEXTA in combination with decitabine, azacitidine, or low-dose cytarabine in patients in M14-358, VIALE-A, and VIALE-C. In this safety population, the most common adverse reactions (≥30% in any trial) were nausea, diarrhea, thrombocytopenia, constipation, neutropenia, febrile neutropenia, fatigue, vomiting, edema, pyrexia, pneumonia, dyspnea, hemorrhage, anemia, rash, abdominal pain, sepsis, musculoskeletal pain, dizziness, cough, oropharyngeal pain, and hypotension.

Chronic Lymphocytic Leukemia/Small Lymphocytic Lymphoma

VENCLEXTA in Combination with Acalabrutinib

The safety of VENCLEXTA in combination with acalabrutinib (VEN+A) (N=291) versus fludarabine plus cyclophosphamide plus rituximab or bendamustine plus rituximab (FCR/BR) (N=259) was evaluated in AMPLIFY, a randomized, multicenter, open-label study in patients with previously untreated CLL [see Clinical Studies (14.1)]. The median duration of exposure to VENCLEXTA was 11.1 months (range: 2 to 14 months) and to acalabrutinib was 12.9 months (range: 1 to 18 months) in the VEN+A arm. Among patients who received VEN+A, 96% were exposed for 6 months or longer and 91% were exposed for greater than one year.

Serious adverse reactions were reported in 25% of patients receiving VEN+A. The most common adverse reaction (≥2%) were COVID-19 including COVID-19 pneumonia (9%), second primary malignancies (2.7%), and neutropenia (2.1%). Fatal adverse events occurred in 3.4% of patients. The most common fatal adverse events included COVID-19 and COVID-19 pneumonia.

In the VEN+A arm, adverse reactions led to treatment discontinuation in 8% of patients. Neutropenia led to discontinuation of VENCLEXTA in 0.3% of patients, dose reduction in 7%, and dose interruption in 21%.

Table 10 presents adverse reactions identified in AMPLIFY.

Table 10. Adverse Reactions (≥15% Any Grade) in Patients with Previously Untreated CLL Who Received VEN+A in AMPLIFY
Body System Adverse Reactions* | VENCLEXTA plus acalabrutinib (N = 291) |  | Investigator’s choice of FCR or BR (N = 259)
 | All Grades (%) | Grade 3 or 4 (%) | All Grades (%) | Grade 3 or 4 (%)
Nervous system disorders
Headache | 35 | 1.4 | 8 | 0.4
Gastrointestinal disorders
Diarrhea | 33 | 1.7 | 11 | 0.4
Nausea | 15 | 0 | 36 | 0
Musculoskeletal and connective tissue disorders
Musculoskeletal paina | 25 | 0.7 | 14 | 0.8
Infections
COVID-19 | 21 | 6 | 3.9 | 1.5
General disorders
Fatigueb | 18 | 0.3 | 17 | 1.5
Skin and subcutaneous tissue disorders
Bruisingc | 17 | 0 | 1.5 | 0
Rashd | 16 | 1 | 16 | 1.5
*Excludes laboratory terms.
a Includes back pain, bone pain, musculoskeletal chest pain, musculoskeletal pain, musculoskeletal discomfort, myalgia, neck pain, pain in extremity, spinal pain, non-cardiac chest pain and pain in jaw.
b Includes fatigue and asthenia.
c Includes increased tendency to bruise, contusion, and ecchymosis.
d Includes rash, dermatitis, and other related terms.

Other clinically relevant adverse reactions reported in <15% of patients receiving VEN+A included upper respiratory tract infections, lower respiratory tract infection, arthralgia, pneumonia, hemorrhage, dizziness, constipation, vomiting, second primary malignancy and hypertension.

Table 11 presents laboratory abnormalities in AMPLIFY.

Table 11. New or Worsening Clinically Important Laboratory Abnormalities (≥15% Any Grade) in Patients with Previously Untreated CLL Who Received VEN+A in AMPLIFY
Laboratory Abnormality | VENCLEXTA plus acalabrutiniba |  | Investigator’s choice of FCR or BRa
 | All grade (%) | Grade 3 or 4 (%) | All grade (%) | Grade 3 or 4 (%)
Hematology
Neutropenia | 78 | 38 | 80 | 53
Lymphopenia | 56 | 12 | 92 | 73
Thrombocytopenia | 43 | 5 | 59 | 15
Anemia | 35 | 7 | 56 | 8
Chemistry
Glucose increased | 74 | 0 | 84 | 0
Calcium decreased | 30 | 0.7 | 25 | 2.3
ALT increased | 26 | 3.1 | 28 | 1.6
Urate increased | 25 | 25 | 23 | 23
LDH increased | 24 | 0 | 40 | 0
Potassium increased | 22 | 2.4 | 12 | 3.1
AST increased | 22 | 1.4 | 28 | 1.6
ALP increased | 20 | 0 | 15 | 0
Glucose decreased | 20 | 0.3 | 5 | 0
Creatinine increased | 19 | 0.3 | 12 | 0.8
Sodium increased | 15 | 0.3 | 9 | 0.4
aThe denominator used to calculate the rate varied between 256 and 290 based on the number of patients with a baseline value and at least one post-treatment value.

Grade 4 laboratory abnormalities that developed in ≥15% of patients treated with VEN+A include absolute neutrophil count decreased (15%).

VENCLEXTA in Combination with Obinutuzumab

The safety of VENCLEXTA in combination with obinutuzumab (VEN+G) (N=212) versus obinutuzumab in combination with chlorambucil (GClb) (N=214) was evaluated in CLL14, a randomized, open-label, actively controlled trial in patients with previously untreated CLL [see Clinical Studies (14.1)]. Patients randomized to the VEN+G arm were treated with VENCLEXTA and obinutuzumab in combination for six cycles, then with VENCLEXTA as monotherapy for an additional six cycles. Patients initiated the first dose of the 5-week ramp-up for VENCLEXTA on Day 22 of Cycle 1 and once completed, continued VENCLEXTA 400 mg orally once daily for a total of 12 cycles. The trial required a total Cumulative Illness Rating Scale (CIRS) >6 or CLcr <70 mL/min, hepatic transaminases and total bilirubin ≤2 times upper limit of normal and excluded patients with any individual organ/system impairment score of 4 by CIRS except eye, ear, nose, and throat organ system. The median duration of exposure to VENCLEXTA was 10.5 months (range: 0 to 13.5 months) and the median number of cycles of obinutuzumab was 6 in the VEN+G arm.

Serious adverse reactions were reported in 49% of patients in the VEN+G arm, most often due to febrile neutropenia and pneumonia (5% each). Fatal adverse reactions that occurred in the absence of disease progression and with onset within 28 days of the last study treatment were reported in 2% (4/212) of patients, most often from infection.

In the VEN+G arm, adverse reactions led to treatment discontinuation in 16% of patients, dose reduction in 21%, and dose interruption in 74%. Neutropenia led to discontinuation of VENCLEXTA in 2% of patients, dose reduction in 13%, and dose interruption in 41%.

Table 12 presents adverse reactions identified in CLL14.

Table 12. Adverse Reactions (≥10%) in Patients Treated with VEN+G in CLL14
Adverse Reaction | VENCLEXTA + Obinutuzumab (N = 212) |  | Obinutuzumab + Chlorambucil (N = 214)
 | All Grades (%) | Grade ≥3 (%) | All Grades (%) | Grade ≥3 (%)
Blood and lymphatic system disorders
Neutropeniaa | 60 | 56 | 62 | 52
Anemiaa | 17 | 8 | 20 | 7
Gastrointestinal disorders
Diarrhea | 28 | 4 | 15 | 1
Nausea | 19 | 0 | 22 | 1
Constipation | 13 | 0 | 9 | 0
Vomiting | 10 | 1 | 8 | 1
General disorders and administration site conditions
Fatiguea | 21 | 2 | 23 | 1
Infections and infestations
Upper respiratory tract infectiona | 17 | 1 | 17 | 1
aIncludes multiple adverse reaction terms.

Other clinically important adverse reactions (All Grades) reported in <10% of patients treated with VEN+G are presented below:

Blood and lymphatic system disorders: febrile neutropenia (6%)

Infection and infestations (all include multiple adverse reaction terms): pneumonia (9%), urinary tract infection (6%), sepsis (4%)

Metabolism and nutrition disorder: tumor lysis syndrome (1%)

During treatment with VENCLEXTA monotherapy after completion of VEN+G, the adverse reaction that occurred in ≥10% of patients was neutropenia (26%). The grade ≥3 adverse reactions that occurred in ≥2% of patients were neutropenia (23%) and anemia (2%).

Table 13 presents laboratory abnormalities CLL14.

Table 13. New or Worsening Clinically Important Laboratory Abnormalities (≥10%) in Patients Treated with VEN+G in CLL14
Laboratory Abnormalitya | VENCLEXTA + Obinutuzumab (N = 212) |  | Obinutuzumab + Chlorambucil (N = 214)
 | All Grades (%) | Grade 3 or 4 (%) | All Grades (%) | Grade 3 or 4 (%)
Hematology
Leukopenia | 90 | 46 | 89 | 41
Lymphopenia | 87 | 57 | 87 | 51
Neutropenia | 83 | 63 | 79 | 56
Thrombocytopenia | 68 | 28 | 71 | 26
Anemia | 53 | 15 | 46 | 11
Chemistry
Blood creatinine increased | 80 | 6 | 74 | 2
Hypocalcemia | 67 | 9 | 58 | 4
Hyperkalemia | 41 | 4 | 35 | 3
Hyperuricemia | 38 | 38 | 38 | 38
aIncludes laboratory abnormalities that were new or worsening, or with worsening from baseline unknown.

Grade 4 laboratory abnormalities that developed in ≥2% of patients treated with VEN+G included neutropenia (32%), leukopenia and lymphopenia (10%), thrombocytopenia (8%), hypocalcemia (8%), hyperuricemia (7%), blood creatinine increased (3%), hypercalcemia (3%), and hypokalemia (2%).

VENCLEXTA in Combination with Rituximab

The safety of VENCLEXTA in combination with rituximab (VEN+R) (N=194) versus bendamustine in combination with rituximab (B+R) (N=188) was evaluated in MURANO [see Clinical Studies (14.1)]. Patients randomized to VEN+R completed the scheduled ramp-up (5 weeks) and received VENCLEXTA 400 mg once daily, in combination with rituximab for 6 cycles followed by VENCLEXTA monotherapy, for a total of 24 months after ramp-up. At the time of analysis, the median duration of exposure to VENCLEXTA was 22 months and the median number of cycles of rituximab was 6 in the VEN+R arm.

Serious adverse reactions were reported in 46% of patients in the VEN+R arm, with most frequent (≥5%) being pneumonia (9%). Fatal adverse reactions that occurred in the absence of disease progression and within 30 days of the last VENCLEXTA treatment and/or 90 days of last rituximab were reported in 2% (4/194) of patients.

In the VEN+R arm, adverse reactions led to treatment discontinuation in 16% of patients, dose reduction in 15%, and dose interruption in 71%. Neutropenia and thrombocytopenia each led to discontinuation of VENCLEXTA in 3% of patients. Neutropenia led to dose interruption of VENCLEXTA in 46% of patients.

Table 14 presents adverse reactions identified in MURANO.

Table 14. Adverse Reactions (≥10%) in Patients Treated with VEN+R in MURANO
Adverse Reaction | VENCLEXTA + Rituximab (N = 194) |  | Bendamustine + Rituximab (N = 188)
 | All Grades (%) | Grade ≥3 (%) | All Grades (%) | Grade ≥3 (%)
Blood and lymphatic system disorders
Neutropeniaa | 65 | 62 | 50 | 44
Anemiaa | 16 | 11 | 23 | 14
Gastrointestinal disorders
Diarrhea | 40 | 3 | 17 | 1
Nausea | 21 | 1 | 34 | 1
Constipation | 14 | <1 | 21 | 0
Infections and infestations
Upper respiratory tract infectiona | 39 | 2 | 23 | 2
Lower respiratory tract infectiona | 18 | 2 | 10 | 2
Pneumoniaa | 10 | 7 | 14 | 10
General disorders and administration site conditions
Fatiguea | 22 | 2 | 26 | <1
aIncludes multiple adverse reaction terms.

Other clinically important adverse reactions (All Grades) reported in <10% of patients treated with VEN+R are presented below:

Blood and lymphatic system disorders: febrile neutropenia (4%)

Gastrointestinal disorders: vomiting (8%)

Infections and infestations: sepsis (<1%)

Metabolism and nutrition disorders: tumor lysis syndrome (3%)

During treatment with VENCLEXTA monotherapy after completion of VEN+R combination treatment, adverse reactions that occurred in ≥10% of patients were upper respiratory tract infection (21%), diarrhea (19%), neutropenia (16%), and lower respiratory tract infections (11%). The Grade 3 or 4 adverse reactions that occurred in ≥2% of patients were neutropenia (12%) and anemia (3%).

Table 15 presents laboratory abnormalities identified in MURANO.

Table 15. New or Worsening Clinically Important Laboratory Abnormalities (≥10%) in Patients Treated with VEN+R in MURANO
Laboratory Abnormality | VENCLEXTA + Rituximab (N = 194) |  | Bendamustine + Rituximab (N = 188)
 | All Gradesa (%) | Grade 3 or 4 (%) | All Gradesa (%) | Grade 3 or 4 (%)
Hematology
Leukopenia | 89 | 46 | 81 | 35
Lymphopenia | 87 | 56 | 79 | 55
Neutropenia | 86 | 64 | 84 | 59
Anemia | 50 | 12 | 63 | 15
Thrombocytopenia | 49 | 15 | 60 | 20
Chemistry
Blood creatinine increased | 77 | <1 | 78 | 1
Hypocalcemia | 62 | 5 | 51 | 2
Hyperuricemia | 36 | 36 | 33 | 33
Hyperkalemia | 24 | 3 | 19 | 2
aIncludes laboratory abnormalities that were new or worsening, or with worsening from baseline unknown.

Grade 4 laboratory abnormalities that developed in ≥2% of patients treated with VEN+R included neutropenia (31%), lymphopenia (16%), leukopenia (6%), thrombocytopenia (6%), hyperuricemia (4%), hypocalcemia (2%), hypoglycemia (2%), and hypermagnesemia (2%).

VENCLEXTA as Monotherapy

The safety of VENCLEXTA was evaluated in pooled data from three single-arm trials (M13-982, M14-032, and M12-175). Patients received VENCLEXTA 400 mg orally once daily after completing the ramp-up phase (N=352). The median duration of treatment with VENCLEXTA at the time of data analysis was 14.5 months (range: 0 to 50 months). Fifty-two percent of patients received VENCLEXTA for more than 60 weeks.

In the pooled dataset, the median age was 66 years (range: 28 to 85 years), 93% were White, and 68% were male. The median number of prior therapies was 3 (range: 0 to 15).

Serious adverse reactions were reported in 52% of patients, with the most frequent (≥5%) being pneumonia (9%), febrile neutropenia (5%), and sepsis (5%). Fatal adverse reactions that occurred in the absence of disease progression and within 30 days of venetoclax treatment were reported in 2% of patients in the VENCLEXTA monotherapy studies, most often (2 patients) from septic shock.

Adverse reactions led to treatment discontinuation in 9% of patients, dose reduction in 13%, and dose interruption in 36%. The most frequent adverse reactions leading to drug discontinuation were thrombocytopenia and autoimmune hemolytic anemia. The most frequent adverse reaction (≥5%) leading to dose reductions or interruptions was neutropenia (8%).

Table 16 presents adverse reactions identified in these trials.

Table 16. Adverse Reactions Reported in ≥10% (All Grades) or ≥5% (Grade ≥3) of Patients with Previously Treated CLL/SLL Who Received VENCLEXTA Monotherapy
Adverse Reaction | VENCLEXTA (N = 352)
 | All Grades (%) | Grade ≥3 (%)
Blood and lymphatic system disorders
Neutropeniaa | 50 | 45
Anemiaa | 33 | 18
Thrombocytopeniaa | 29 | 20
Lymphopeniaa | 11 | 7
Febrile neutropenia | 6 | 6
Gastrointestinal disorders
Diarrhea | 43 | 3
Nausea | 42 | 1
Abdominal paina | 18 | 3
Vomiting | 16 | 1
Constipation | 16 | <1
Mucositisa | 13 | <1
Infections and infestations
Upper respiratory tract infectiona | 36 | 1
Pneumoniaa | 14 | 8
Lower respiratory tract infectiona | 11 | 2
General disorders and administration site conditions
Fatiguea | 32 | 4
Edemaa | 22 | 2
Pyrexia | 18 | <1
Musculoskeletal and connective tissue disorders
Musculoskeletal paina | 29 | 2
Arthralgia | 12 | <1
Respiratory, thoracic, and mediastinal disorders
Cougha | 22 | 0
Dyspneaa | 13 | 1
Nervous system disorders
Headache | 18 | <1
Dizzinessa | 14 | 0
Skin and subcutaneous tissue disorders
Rasha | 18 | <1
Adverse reactions graded using NCI Common Terminology Criteria for Adverse Events version 4.0.
aIncludes multiple adverse reaction terms.

Table 17 presents laboratory abnormalities reported throughout treatment that were new or worsening from baseline. The most common (>5%) Grade 4 laboratory abnormalities observed with VENCLEXTA monotherapy were hematologic laboratory abnormalities, including neutropenia (33%), leukopenia (11%), thrombocytopenia (15%), and lymphopenia (9%).

Table 17. New or Worsening Laboratory Abnormalities in ≥40% (All Grades) or ≥10% (Grade 3 or 4) of Patients with Previously Treated CLL/SLL Who Received VENCLEXTA Monotherapy
Laboratory Abnormality | VENCLEXTA (N = 352)
 | All Gradesa (%) | Grade 3 or 4 (%)
Hematology
Leukopenia | 89 | 42
Neutropenia | 87 | 63
Lymphopenia | 74 | 40
Anemia | 71 | 26
Thrombocytopenia | 64 | 31
Chemistry
Hypocalcemia | 87 | 12
Hyperglycemia | 67 | 7
Hyperkalemia | 59 | 5
AST increased | 53 | 3
Hypoalbuminemia | 49 | 2
Hypophosphatemia | 45 | 11
Hyponatremia | 40 | 9
aIncludes laboratory abnormalities that were new or worsening, or worsening from baseline unknown.

Important Adverse Reactions in CLL/SLL

Tumor Lysis Syndrome

Tumor lysis syndrome is an important identified risk when initiating VENCLEXTA.

CLL14

The incidence of TLS was 1% (3/212) in patients treated with VEN+G [see Warnings and Precautions (5.1)]. All three events of TLS resolved and did not lead to withdrawal from the trial. Obinutuzumab administration was delayed in two cases in response to the TLS events.

MURANO

The incidence of TLS was 3% (6/194) in patients treated with VEN+R. After 77/389 patients were enrolled in the trial, the protocol was amended to incorporate the current TLS prophylaxis and monitoring measures described in sections 2.2 and 2.4 [see Dosage and Administration (2.2, 2.4)]. All events of TLS occurred during the VENCLEXTA ramp-up period and were resolved within two days. All six patients completed the ramp-up and reached the recommended daily dose of 400 mg of VENCLEXTA. No clinical TLS was observed in patients who followed the current 5-week ramp-up schedule and TLS prophylaxis and monitoring measures [see Dosage and Administration (2.2, 2.4)]. Rates of laboratory abnormalities relevant to TLS for patients treated with VEN+R are presented in Table 14.

Monotherapy Studies (M13-982 and M14-032)

In 168 patients with CLL treated according to recommendations described in sections 2.1 and 2.2, the rate of TLS was 2% [see Dosage and Administration (2.2, 2.4)]. All events either met laboratory TLS criteria (laboratory abnormalities that met ≥2 of the following within 24 hours of each other: potassium >6 mmol/L, uric acid >476 µmol/L, calcium <1.75 mmol/L, or phosphorus >1.5 mmol/L), or were reported as TLS events. The events occurred in patients who had a lymph node(s) ≥5 cm and/or absolute lymphocyte count (ALC) ≥25 x 10^9/L. All events resolved within 5 days. No TLS with clinical consequences such as acute renal failure, cardiac arrhythmias, or sudden death and/or seizures was observed in these patients. All patients had CLcr ≥50 mL/min. Laboratory abnormalities relevant to TLS were hyperkalemia (17% all Grades, 1% Grade ≥3), hyperphosphatemia (14% all Grades, 2% Grade ≥3), hypocalcemia (16% all Grades, 2% Grade ≥3), and hyperuricemia (10% all Grades, <1% Grade ≥3).

In the initial Phase 1 dose-finding trials, which had shorter (2-3 week) ramp-up phase and higher starting doses, the incidence of TLS was 13% (10/77; 5 laboratory TLS, 5 clinical TLS), including 2 fatal events and 3 events of acute renal failure, 1 requiring dialysis. After this experience, TLS risk assessment, dosing regimen, TLS prophylaxis and monitoring measures were revised [see Dosage and Administration (2.2, 2.4)].

Acute Myeloid Leukemia

VENCLEXTA in Combination with Azacitidine

The safety of VENCLEXTA in combination with azacitidine (VEN+AZA) (N=283) versus placebo in combination with azacitidine (PBO+AZA) (N=144) was evaluated in VIALE-A, a double-blind, randomized trial, in patients with newly diagnosed AML [see Clinical Studies (14.2)]. At baseline, patients were ≥75 years of age or had comorbidities that precluded the use of intensive induction chemotherapy based on at least one of the following criteria: baseline ECOG performance status of 2-3, severe cardiac or pulmonary comorbidity, moderate hepatic impairment, CLcr <45 mL/min, or other comorbidity. Patients were randomized to receive VENCLEXTA 400 mg orally once daily after completion of the ramp-up phase in combination with azacitidine (75 mg/m^2 either intravenously or subcutaneously on Days 1-7 of each 28-day cycle) or placebo in combination with azacitidine. Among patients who received VEN+AZA, the median duration of exposure to VENCLEXTA was 7.6 months (range: <0.1 to 30.7 months).

Serious adverse reactions were reported in 83% of patients who received VEN+AZA, with the most frequent (≥5%) being febrile neutropenia (30%), pneumonia (22%), sepsis (excluding fungal; 19%), and hemorrhage (6%). Fatal adverse reactions occurred in 23% of patients who received VEN+AZA, with the most frequent (≥2%) being pneumonia (4%), sepsis (excluding fungal; 3%), and hemorrhage (2%).

Adverse reactions led to permanent discontinuation of VENCLEXTA in 24% of patients, dose reductions in 2%, and dose interruptions in 72%. Adverse reactions which led to discontinuation of VENCLEXTA in ≥2% of patients were sepsis (excluding fungal; 3%) and pneumonia (2%). The most frequent adverse reaction leading to dose reduction was pneumonia (0.7%). Adverse reactions which required a dose interruption in ≥5% of patients included febrile neutropenia (20%), neutropenia (20%), pneumonia (14%), sepsis (excluding fungal; 11%), and thrombocytopenia (10%). Among patients who achieved bone marrow clearance of leukemia, 53% underwent dose interruptions for absolute neutrophil count (ANC) <500/microliter.

Table 18 presents adverse reactions identified in VIALE-A.

Table 18. Adverse Reactions (≥10%) in Patients with AML Who Received VEN+AZA with a Difference Between Arms of ≥5% for All Grades or ≥2% for Grade 3 or 4 Reactions Compared with PBO+AZA in VIALE-A
Adverse Reaction | VENCLEXTA + Azacitidine (N = 283) |  | Placebo + Azacitidine (N = 144)
 | All Grades (%) | Grade 3 or 4 (%) | All Grades (%) | Grade 3 or 4 (%)
Gastrointestinal disorders
Nausea | 44 | 2 | 35 | <1
Diarrheaa | 43 | 5 | 33 | 3
Vomitingb | 30 | 2 | 23 | <1
Stomatitisc | 18 | 1 | 13 | 0
Abdominal paind | 18 | <1 | 13 | 0
Blood and lymphatic system disorders
Febrile neutropenia | 42 | 42 | 19 | 19
Musculoskeletal and connective tissue disorders
Musculoskeletal paine | 36 | 2 | 28 | 1
General disorders and administration site conditions
Fatiguef | 31 | 6 | 23 | 2
Edemag | 27 | <1 | 19 | 0
Vascular disorders
Hemorrhageh | 27 | 7 | 24 | 3
Hypotensioni | 12 | 5 | 8 | 3
Metabolism and nutrition disorders
Decreased appetitej | 25 | 4 | 17 | <1
Skin and subcutaneous tissue disorders
Rashk | 25 | 1 | 15 | 0
Infections and infestations
Sepsisl (excluding fungal) | 22 | 22 | 16 | 14
Urinary tract infectionm | 16 | 6 | 9 | 6
Respiratory, thoracic and mediastinal disorders
Dyspnean | 18 | 4 | 10 | 2
Nervous system disorders
Dizzinesso | 17 | <1 | 8 | <1
aIncludes diarrhea and colitis.
bIncludes vomiting and hematemesis.
cIncludes stomatitis, mouth ulceration, mucosal inflammation, cheilitis, aphthous ulcer, glossitis, and tongue ulceration.
dIncludes abdominal pain, abdominal pain upper, abdominal discomfort, and abdominal pain lower.
eIncludes arthralgia, back pain, pain in extremity, musculoskeletal pain, bone pain, myalgia, neck pain, non-cardiac chest pain, arthritis, musculoskeletal chest pain, musculoskeletal stiffness, spinal pain, and musculoskeletal discomfort.
fIncludes fatigue and asthenia.
gIncludes edema peripheral, edema, generalized edema, eyelid edema, face edema, penile edema, periorbital edema, and swelling.
hIncludes epistaxis, hematuria, conjunctival hemorrhage, hemoptysis, hemorrhoidal hemorrhage, gingival bleeding, mouth hemorrhage, hemorrhage intracranial, vaginal hemorrhage, cerebral hemorrhage, gastrointestinal hemorrhage, muscle hemorrhage, skin hemorrhage, upper gastrointestinal hemorrhage, anal hemorrhage, eye hemorrhage, gastritis hemorrhagic, hemorrhage, hemorrhage urinary tract, hemorrhagic diathesis, hemorrhagic stroke, hemorrhagic vasculitis, lower gastrointestinal hemorrhage, mucosal hemorrhage, penile hemorrhage, post procedural hemorrhage, rectal hemorrhage, retinal hemorrhage, shock hemorrhagic, soft tissue hemorrhage, subdural hemorrhage, tongue hemorrhage, urethral hemorrhage, vessel puncture site hemorrhage, vitreous hemorrhage, and wound hemorrhage.
iIncludes hypotension and orthostatic hypotension.
jIncludes decreased appetite and hypophagia.
kIncludes rash, rash maculo-papular, rash macular, drug eruption, rash papular, rash pustular, eczema, rash erythematous, rash pruritic, dermatitis acneiform, rash morbilliform, dermatitis, eczema asteatotic, exfoliative rash, and perivascular dermatitis.
lIncludes sepsis, escherichia bacteremia, escherichia sepsis, septic shock, bacteremia, staphylococcal bacteremia, klebsiella bacteremia, staphylococcal sepsis, streptococcal bacteremia, enterococcal bacteremia, klebsiella sepsis, pseudomonal bacteremia, pseudomonal sepsis, urosepsis, bacterial sepsis, clostridial sepsis, enterococcal sepsis, neutropenic sepsis, and streptococcal sepsis.
mIncludes urinary tract infection, escherichia urinary tract infection, cystitis, urinary tract infection enterococcal, urinary tract infection bacterial, pyelonephritis acute, and urinary tract infection pseudomonal.
nIncludes dyspnea, dyspnea exertional, and dyspnea at rest.
oIncludes dizziness and vertigo.

Other clinically important adverse reactions (All Grades) at ≥10% that did not meet criteria for Table 18 or <10% are presented below:

Hepatobiliary disorders: cholecystitis/cholelithiasisa (4%)

Infections and infestations: pneumoniab (33%)

Metabolism and nutrition disorders: tumor lysis syndrome (1%)

Nervous system disorders: headachec (11%)

Investigations: weight decreased (13%).

aIncludes cholecystitis acute, cholelithiasis, cholecystitis, and cholecystitis chronic.
bIncludes pneumonia, lung infection, pneumonia fungal, pneumonia klebsiella, atypical pneumonia, lower respiratory tract infection, pneumonia viral, lower respiratory tract infection fungal, pneumonia hemophilus, pneumonia pneumococcal, and pneumonia respiratory syncytial viral.
cIncludes headache and tension headache.

Table 19 presents laboratory abnormalities identified in VIALE-A.

Table 19. New or Worsening Laboratory Abnormalities (≥10%) in Patients with AML Who Received VEN+AZA with a Difference Between Arms of ≥5% for All Grades or ≥2% for Grade 3 or 4 Reactions Compared with PBO+AZA in VIALE-A
Laboratory Abnormality | VENCLEXTA + Azacitidine |  | Placebo + Azacitidine
 | All Grades (%) | Grade 3 or 4 (%) | All Grades (%) | Grade 3 or 4 (%)
Hematology
Neutrophils decreased | 98 | 98 | 88 | 81
Platelet decreased | 94 | 88 | 94 | 80
Lymphocytes decreased | 91 | 71 | 72 | 39
Hemoglobin decreased | 61 | 57 | 56 | 52
Chemistry
Bilirubin increased | 53 | 7 | 40 | 4
Calcium decreased | 51 | 6 | 39 | 9
Sodium decreased | 46 | 14 | 47 | 8
Alkaline phosphatase increased | 42 | 1 | 29 | <1
Blood bicarbonate decreased | 31 | <1 | 25 | 0
The denominator used to calculate the rate varied from 85 to 144 in the PBO+AZA arm and from 125 to 283 in the VEN+AZA arm based on the number of patients with at least one post-treatment value.

VENCLEXTA in Combination with Azacitidine or Decitabine

The safety of VENCLEXTA in combination with azacitidine (N=67) or decitabine (N=13) was evaluated in M14-358, a non-randomized trial of patients with newly diagnosed AML. At baseline, patients were ≥75 years of age, or had comorbidities that precluded the use of intensive induction chemotherapy based on at least one of the following criteria: baseline ECOG performance status of 2-3, severe cardiac or pulmonary comorbidity, moderate hepatic impairment, CLcr <45 mL/min, or other comorbidity [see Clinical Studies (14.2)]. Patients received VENCLEXTA 400 mg orally once daily after completion of the ramp-up phase in combination with azacitidine (75 mg/m^2 either intravenously or subcutaneously on Days 1-7 of each 28-day cycle) or decitabine (20 mg/m^2 intravenously on Days 1-5 of each 28-day cycle).

Azacitidine

The median duration of exposure to VENCLEXTA when administered in combination with azacitidine was 6.5 months (range: 0.1 to 38.1 months). The safety of VENCLEXTA in combination with azacitidine in this trial is consistent with that of VIALE-A.

Decitabine

The median duration of exposure to VENCLEXTA when administered in combination with decitabine was 8.4 months (range: 0.5 to 39 months).

Serious adverse reactions were reported in 85% of patients who received VENCLEXTA with decitabine, the most frequent (≥10%) being sepsis (excluding fungal; 46%), febrile neutropenia (38%), and pneumonia (31%). One (8%) fatal adverse reaction of bacteremia occurred within 30 days of starting treatment.

Permanent discontinuation of VENCLEXTA due to adverse reactions occurred in 38% of patients. The most frequent adverse reaction leading to permanent discontinuation (≥5%) was pneumonia (8%).

Dosage reductions of VENCLEXTA due to adverse reactions occurred in 15% of patients. The most frequent adverse reaction leading to dose reduction (≥5%) was neutropenia (15%).

Dosage interruptions of VENCLEXTA due to adverse reactions occurred in 69% of patients. The most frequent adverse reactions leading to dose interruption (≥10%) were neutropenia (38%), febrile neutropenia (23%), leukopenia (15%), and pneumonia (15%).

The most common adverse reactions (≥30%) were febrile neutropenia (69%), fatigue (62%), constipation (62%), musculoskeletal pain (54%), dizziness (54%), nausea (54%), abdominal pain (46%), diarrhea (46%), pneumonia (46%), sepsis (excluding fungal; 46%), cough (38%), pyrexia (31%), hypotension (31%), oropharyngeal pain (31%), edema (31%), and vomiting (31%). The most common laboratory abnormalities (≥30%) were neutrophils decreased (100%), lymphocytes decreased (100%), white blood cells decreased (100%), platelets decreased (92%), calcium decreased (85%), hemoglobin decreased (69%), glucose increased (69%), magnesium decreased (54%), potassium decreased (46%), bilirubin increased (46%), albumin decreased (38%), alkaline phosphatase increased (38%), sodium decreased (38%), ALT increased (31%), creatinine increased (31%), and potassium increased (31%).

VENCLEXTA in Combination with Low-Dose Cytarabine

VIALE-C

The safety of VENCLEXTA in combination with low-dose cytarabine (VEN+LDAC) (N=142) versus placebo with low-dose cytarabine (PBO+LDAC) (N=68) was evaluated in VIALE-C, a double-blind randomized trial in patients with newly diagnosed AML. At baseline, patients were ≥75 years of age, or had comorbidities that precluded the use of intensive induction chemotherapy based on at least one of the following criteria: baseline ECOG performance status of 2-3, severe cardiac or pulmonary comorbidity, moderate hepatic impairment, CLcr <45 mL/min, or other comorbidity [see Clinical Studies (14.2)]. Patients were randomized to receive VENCLEXTA 600 mg orally once daily after completion of a 4-day ramp-up phase in combination with low-dose cytarabine (20 mg/m^2 subcutaneously once daily on Days 1-10 of each 28-day cycle) or placebo in combination with low-dose cytarabine. Among patients who received VEN+LDAC, the median duration of exposure to VENCLEXTA was 3.9 months (range: <0.1 to 17.1 months).

Serious adverse reactions were reported in 65% of patients who received VEN+LDAC, with the most frequent (≥10%) being pneumonia (17%), febrile neutropenia (16%), and sepsis (excluding fungal; 12%). Fatal adverse reactions occurred in 23% of patients who received VEN+LDAC, with the most frequent (≥5%) being pneumonia (6%) and sepsis (excluding fungal; 7%).

Adverse reactions led to permanent discontinuation of VENCLEXTA in 25% of patients, dose reductions in 9%, and dose interruptions in 63%. The most frequent adverse reaction (>2%) which resulted in permanent discontinuation of VENCLEXTA was pneumonia (6%). Adverse reactions which required a dose reduction in ≥1% of patients were pneumonia (1%) and thrombocytopenia (1%), and the adverse reactions which required a dose interruption in ≥5% of patients included neutropenia (20%), thrombocytopenia (15%), pneumonia (8%), febrile neutropenia (6%), and sepsis (excluding fungal; 6%). Among patients who achieved bone marrow clearance of leukemia, 32% underwent dose interruptions for ANC <500/microliter.

Table 20 presents adverse reactions identified in VIALE-C.

Table 20. Adverse Reactions (≥10%) in Patients with AML Who Received VEN+LDAC with a Difference Between Arms of ≥5% for All Grades or ≥2% for Grade 3 or 4 Compared with PBO+LDAC in VIALE-C
Adverse Reaction | VENCLEXTA + Low-Dose Cytarabine (N = 142) |  | Placebo + Low-Dose Cytarabine (N = 68)
 | All Grades (%) | Grade 3 or 4 (%) | All Grades (%) | Grade 3 or 4 (%)
Gastrointestinal disorders
Nausea | 42 | 1 | 31 | 0
Diarrhea | 28 | 3 | 16 | 0
Vomiting | 25 | <1 | 13 | 0
Abdominal paina | 15 | <1 | 9 | 3
Stomatitisb | 15 | 1 | 6 | 0
Blood and lymphatic system disorders
Febrile neutropenia | 32 | 32 | 29 | 29
Infections and infestations
Pneumoniac | 29 | 19 | 21 | 21
Vascular Disorders
Hemorrhaged | 27 | 8 | 16 | 1
Hypotensione | 11 | 5 | 4 | 1
Musculoskeletal and connective tissue disorders
Musculoskeletal painf | 23 | 3 | 18 | 0
General Disorders and Administration Site Conditions
Fatigueg | 22 | 2 | 21 | 0
Nervous System Disorders
Headache | 11 | 0 | 6 | 0
aIncludes abdominal pain, abdominal pain upper, abdominal discomfort, and abdominal pain lower.
bIncludes stomatitis, mouth ulceration, aphthous ulcer, glossitis, mucosal inflammation, and tongue ulceration.
cIncludes pneumonia, lung infection, lower respiratory tract infection, pneumonia fungal, lower respiratory tract infection fungal, pneumocystis jirovecii pneumonia, pneumonia aspiration, pneumonia cytomegaloviral, and pneumonia pseudomonal.
dIncludes epistaxis, conjunctival hemorrhage, hemoptysis, gastrointestinal hemorrhage, gingival bleeding, mouth hemorrhage, upper gastrointestinal hemorrhage, hematuria, retinal hemorrhage, catheter site hemorrhage, cerebral hemorrhage, gastric hemorrhage, gastritis hemorrhagic, hemorrhage intracranial, hemorrhage subcutaneous, lip hemorrhage, mucosal hemorrhage, pharyngeal hemorrhage, post procedural hemorrhage, pulmonary alveolar hemorrhage, pulmonary hemorrhage, tooth pulp hemorrhage, uterine hemorrhage, and vascular access site hemorrhage.
eIncludes hypotension and orthostatic hypotension.
fIncludes back pain, arthralgia, pain in extremity, musculoskeletal pain, myalgia, neck pain, non-cardiac chest pain, arthritis, bone pain, musculoskeletal chest pain, and spinal pain.
gIncludes fatigue and asthenia.

Other clinically important adverse reactions (All Grades) at ≥10% that did not meet criteria for Table 20 or <10% are presented below:

Hepatobiliary disorders: cholecystitis/cholelithiasisa (1%)

Infections and infestations: sepsisb (excluding fungal; 15%), urinary tract infectionc (8%)

Metabolism and nutrition disorders: decreased appetite (19%), tumor lysis syndrome (6%)

Nervous system disorders: dizzinessd (9%)

Respiratory, thoracic, and mediastinal disorders: dyspneae (10%)

Investigations: weight decreased (9%).

aIncludes cholecystitis and cholecystitis acute.
bIncludes sepsis, bacteremia, septic shock, neutropenic sepsis, staphylococcal bacteremia, streptococcal bacteremia, bacterial sepsis, Escherichia bacteremia, pseudomonal bacteremia, and staphylococcal sepsis.
cIncludes urinary tract infection and escherichia urinary tract infection.
dIncludes dizziness and vertigo.
eIncludes dyspnea and dyspnea exertional.

Table 21 describes laboratory abnormalities identified in VIALE-C.

Table 21. New or Worsening Laboratory Abnormalities (≥10%) in Patients with AML Who Received VEN+LDAC with Difference Between Arms of ≥5% for All Grades or ≥2% for Grade 3 or 4 Reactions Compared with PBO+LDAC in VIALE-C
Laboratory Abnormality | VENCLEXTA + Low-Dose Cytarabine |  | Placebo + Low-Dose Cytarabine
 | All Grades (%) | Grade 3 or 4 (%) | All Grades (%) | Grade 3 or 4 (%)
Hematology
Platelets decreased | 97 | 95 | 92 | 90
Neutrophils decreased | 95 | 92 | 82 | 71
Lymphocytes decreased | 92 | 69 | 65 | 24
Hemoglobin decreased | 63 | 57 | 57 | 54
Chemistry
Bilirubin increased | 61 | 7 | 38 | 7
Albumin decreased | 61 | 6 | 43 | 4
Potassium decreased | 56 | 16 | 42 | 14
Calcium decreased | 53 | 8 | 45 | 13
Glucose increased | 52 | 13 | 59 | 9
AST increased | 36 | 6 | 37 | 1
Alkaline phosphatase increased | 34 | 1 | 26 | 1
ALT increased | 30 | 4 | 26 | 1
Sodium increased | 11 | 3 | 6 | 1
The denominator used to calculate the rate varied from 38 to 68 in the PBO+LDAC arm and from 65 to 142 in the VEN+LDAC arm based on the number of patients with at least one post-treatment value.

M14-387

The safety of VENCLEXTA in combination with low-dose cytarabine (N=61) was evaluated in M14-387, a non-randomized, open- label trial of patients with newly diagnosed AML [see Clinical Studies (14.2)]. At baseline, patients were ≥75 years of age, or had comorbidities that precluded the use of intensive induction chemotherapy based on at least one of the following criteria: baseline ECOG performance status of 2-3, severe cardiac or pulmonary comorbidity, moderate hepatic impairment, CLcr <45 mL/min, or other comorbidity. Patients received VENCLEXTA 600 mg orally once daily after completion of the ramp-up phase in combination with low-dose cytarabine (20mg/m^2 subcutaneously on Days 1-10 of each 28-day cycle). The safety of VENCLEXTA in combination with low-dose cytarabine is consistent with that of VIALE-C.

7 DRUG INTERACTIONS

7.1 Effects of Other Drugs on VENCLEXTA

Strong or Moderate CYP3A Inhibitors or P-gp Inhibitors

Concomitant use with a strong or moderate CYP3A inhibitor or a P-gp inhibitor increases venetoclax Cmax and AUC0-INF [see Clinical Pharmacology (12.3)], which may increase VENCLEXTA toxicities, including the risk of TLS [see Warnings and Precautions (5.1)].

Concomitant use with a strong CYP3A inhibitor at initiation and during the ramp-up phase in patients with CLL/SLL is contraindicated [see Contraindications (4)].

In patients with CLL/SLL taking a steady daily dosage (after ramp-up phase), consider alternative medications or adjust VENCLEXTA dosage and monitor more frequently for adverse reactions [see Dosage and Administration (2.5, 2.6)].

In patients with AML, adjust VENCLEXTA dosage and monitor more frequently for adverse reactions [see Dosage and Administration (2.5, 2.6)].

Resume the VENCLEXTA dosage that was used prior to concomitant use with a strong or moderate CYP3A inhibitor or a P-gp inhibitor 2 to 3 days after discontinuation of the inhibitor [see Dosage and Administration (2.5, 2.6)].

Avoid grapefruit products, Seville oranges, and starfruit during treatment with VENCLEXTA, as they contain inhibitors of CYP3A.

Strong or Moderate CYP3A Inducers

Concomitant use with a strong CYP3A inducer decreases venetoclax Cmax and AUC0-INF [see Clinical Pharmacology (12.3)], which may decrease VENCLEXTA efficacy. Avoid concomitant use of VENCLEXTA with strong CYP3A inducers or moderate CYP3A inducers.

7.2 Effect of VENCLEXTA on Other Drugs

Warfarin

Concomitant use of VENCLEXTA increases warfarin Cmax and AUC0-INF [see Clinical Pharmacology (12.3)], which may increase the risk of bleeding. Monitor international normalized ratio (INR) more frequently in patients using warfarin concomitantly with VENCLEXTA.

P-gp Substrates

Concomitant use of VENCLEXTA increases Cmax and AUC0-INF of P-gp substrates [see Clinical Pharmacology (12.3)], which may increase toxicities of these substrates. Avoid concomitant use of VENCLEXTA with a P-gp substrate. If a concomitant use is unavoidable, separate dosing of the P-gp substrate at least 6 hours before VENCLEXTA.

8 USE IN SPECIFIC POPULATIONS

8.1 Pregnancy

Risk Summary

Based on findings in animals and its mechanism of action [see Clinical Pharmacology (12.1)], VENCLEXTA may cause embryo-fetal harm when administered to a pregnant woman. There are no available data on VENCLEXTA use in pregnant women to inform a drug-associated risk. Administration of venetoclax to pregnant mice during the period of organogenesis was fetotoxic at exposures 1.2 times the human exposure at the recommended dose of 400 mg daily based on AUC. Advise pregnant women of the potential risk to a fetus.

The estimated background risk of major birth defects and miscarriage for the indicated population is unknown. All pregnancies have a background risk of birth defect, loss, or other adverse outcomes. In the U.S. general population, the estimated background risk of major birth defects and miscarriage in clinically recognized pregnancies is 2% to 4% and 15% to 20%, respectively.

Data

Animal data

In embryo-fetal development studies, venetoclax was administered to pregnant mice and rabbits during the period of organogenesis. In mice, venetoclax was associated with increased post-implantation loss and decreased fetal body weight at 150 mg/kg/day (maternal exposures approximately 1.2 times the human exposure at the recommended dose of 400 mg once daily). No teratogenicity was observed in either the mouse or the rabbit.

8.2 Lactation

Risk Summary

There are no data on the presence of VENCLEXTA in human milk or the effects on the breastfed child or milk production. Venetoclax was present in the milk when administered to lactating rats (see Data).

Because of the potential for serious adverse reactions in a breastfed child, advise women not to breastfeed during treatment with VENCLEXTA and for 1 week after the last dose.

Data

Animal Data

Venetoclax was administered (single dose; 150 mg/kg oral) to lactating rats 8 to 10 days post-parturition. Venetoclax in milk was 1.6 times lower than in plasma. Parent drug (venetoclax) represented the majority of the total drug-related material in milk, with trace levels of three metabolites.

8.3 Females and Males of Reproductive Potential

VENCLEXTA may cause fetal harm when administered to pregnant women [see Use in Specific Populations (8.1)].

Pregnancy Testing

Verify pregnancy status in females of reproductive potential prior to initiating VENCLEXTA.

Contraception

Advise females of reproductive potential to use effective contraception during treatment with VENCLEXTA and for 30 days after the last dose.

Infertility

Based on findings in animals, VENCLEXTA may impair male fertility [see Nonclinical Toxicology (13.1)].

8.4 Pediatric Use

The safety and effectiveness of VENCLEXTA have not been established in pediatric patients.

Juvenile Animal Toxicity Data

In a juvenile toxicology study, mice were administered venetoclax at 10, 30, or 100 mg/kg/day by oral gavage from 7 to 60 days of age. Clinical signs of toxicity included decreased activity, dehydration, skin pallor, and hunched posture at ≥30 mg/kg/day. In addition, mortality and body weight effects occurred at 100 mg/kg/day. Other venetoclax-related effects were reversible decreases in lymphocytes at ≥10 mg/kg/day; a dose of 10 mg/kg/day is approximately 0.06 times the clinical dose of 400 mg on a mg/m^2 basis for a 20 kg child.

8.5 Geriatric Use

Chronic Lymphocytic Leukemia/Small Lymphocytic Lymphoma

Of the 352 patients with previously treated CLL/SLL evaluated for safety from 3 open-label trials of VENCLEXTA monotherapy, 57% (201/352) were ≥65 years of age and 18% (62/352) were ≥75 years of age. Of the 406 patients with CLL/SLL evaluated for safety from VENCLEXTA in combination with rituximab or obinutuzumab, 67% (273/406) were ≥65 years of age and 24% (97/406) were ≥75 years of age. No clinically meaningful differences in safety and effectiveness were observed between older and younger patients in these studies.

Of patients that received VENCLEXTA in combination with acalabrutinib in AMPLIFY, 33% (97/291) were ≥65 years of age, and 4.5% (13/291) were ≥75 years of age. In patients 65 years of age or older and younger than age 65, the fatal adverse reactions were 5% and 2.6%, respectively. No clinically relevant differences in efficacy were observed between patients ≥65 years of age and younger adults.

Acute Myeloid Leukemia

Of the 283 patients who received VENCLEXTA with azacitidine in VIALE-A, 96% were ≥65 years of age and 60% were ≥75 years of age.

Of the 13 patients who received VENCLEXTA in combination with decitabine in M14-358, 100% were ≥65 years of age and 62% were ≥75 years of age.

Of the 142 patients who received VENCLEXTA in combination with low-dose cytarabine in VIALE-C, 92% were ≥65 years of age and 57% were ≥75 years of age.

Clinical studies of VENCLEXTA in patients with AML did not include sufficient numbers of younger adults to determine if patients 65 years of age and older respond differently from younger adults.

8.6 Renal Impairment

Due to the increased risk of TLS, patients with reduced renal function (CLcr <80 mL/min, calculated by Cockcroft-Gault formula) require more intensive prophylaxis and monitoring to reduce the risk of TLS when initiating treatment with VENCLEXTA [see Dosage and Administration (2.1, 2.2, 2.3, 2.4) and Warnings and Precautions (5.1)].

No dose adjustment is recommended for patients with mild, moderate or severe renal impairment (CLcr ≥15 mL/min) [see Clinical Pharmacology (12.3)].

8.7 Hepatic Impairment

No dose adjustment is recommended for patients with mild (Child-Pugh A) or moderate (Child-Pugh B) hepatic impairment.

Reduce the dose of VENCLEXTA for patients with severe hepatic impairment (Child-Pugh C); monitor these patients more frequently for adverse reactions [see Dosage and Administration (2.5, 2.7) and Clinical Pharmacology (12.3)].

10 OVERDOSAGE

There is no specific antidote for VENCLEXTA. For patients who experience overdose, closely monitor and provide appropriate supportive treatment; during ramp-up phase interrupt VENCLEXTA and monitor carefully for signs and symptoms of TLS along with other toxicities [see Dosage and Administration (2.2, 2.3, 2.4, 2.5)]. Based on venetoclax large volume of distribution and extensive protein binding, dialysis is unlikely to result in significant removal of venetoclax.

11 DESCRIPTION

Venetoclax is a BCL-2 inhibitor. It is a light yellow to dark yellow solid with the empirical formula C45H50ClN7O7S and a molecular weight of 868.44. Venetoclax is described chemically as 4-(4-{[2-(4-chlorophenyl)-4,4-dimethylcyclohex-1-en-1-yl]methyl}piperazin-1-yl)-N-({3-nitro-4-[(tetrahydro-2H-pyran-4-ylmethyl)amino]phenyl}sulfonyl)-2-(1H-pyrrolo[2,3-b]pyridin-5-yloxy)benzamide) and has the following chemical structure:

Venetoclax has very low aqueous solubility.

VENCLEXTA tablets for oral use are supplied as pale yellow or beige tablets that contain 10 mg, 50 mg, or 100 mg venetoclax as the active ingredient. Each tablet also contains the following inactive ingredients: copovidone, colloidal silicon dioxide, polysorbate 80, sodium stearyl fumarate, and calcium phosphate dibasic. In addition, the 10 mg and 100 mg coated tablets include the following: iron oxide yellow, polyvinyl alcohol, polyethylene glycol, talc, and titanium dioxide. The 50 mg coated tablets also include the following: iron oxide yellow, iron oxide red, iron oxide black, polyvinyl alcohol, talc, polyethylene glycol and titanium dioxide. Each tablet is debossed with “V” on one side and “10”, “50” or “100” corresponding to the tablet strength on the other side.

12 CLINICAL PHARMACOLOGY

12.1 Mechanism of Action

Venetoclax is a selective and orally bioavailable small-molecule inhibitor of BCL-2, an anti-apoptotic protein. Overexpression of BCL-2 has been demonstrated in CLL and AML cells where it mediates tumor cell survival and has been associated with resistance to chemotherapeutics. Venetoclax helps restore the process of apoptosis by binding directly to the BCL-2 protein, displacing pro-apoptotic proteins like BIM, triggering mitochondrial outer membrane permeabilization and the activation of caspases. In nonclinical studies, venetoclax has demonstrated cytotoxic activity in tumor cells that overexpress BCL-2.

12.2 Pharmacodynamics

Based on the exposure response analyses for efficacy, a relationship between drug exposure and a greater likelihood of response was observed in clinical studies in patients with CLL/SLL, and in patients with AML. Based on the exposure response analyses for safety, a relationship between drug exposure and a greater likelihood of some safety events was observed in clinical studies in patients with AML. No exposure-safety relationship was observed in patients with CLL/SLL at doses up to 1200 mg given as monotherapy and up to 600 mg given in combination with rituximab.

Cardiac Electrophysiology

The effect of multiple doses of VENCLEXTA up to 1200 mg once daily (2 times the maximum approved recommended dosage) on the QTc interval was evaluated in an open-label, single-arm trial in 176 patients with previously treated hematologic malignancies. VENCLEXTA had no large effect on QTc interval (i.e., >20 ms) and there was no relationship between venetoclax exposure and change in QTc interval.

12.3 Pharmacokinetics

Venetoclax mean (± standard deviation) steady state Cmax was 2.1 ± 1.1 mcg/mL and AUC0-24h was 32.8 ± 16.9 mcg•h/mL following administration of 400 mg once daily with a low-fat meal. Venetoclax steady state AUC increased proportionally over the dose range of 150 to 800 mg (0.25 to 1.33 times the maximum approved recommended dosage). The pharmacokinetics of venetoclax does not change over time.

Absorption

Maximum plasma concentration of venetoclax was reached 5 to 8 hours following multiple oral administration under fed conditions.

Effect of Food

Administration with a low-fat meal (approximately 512 kilocalories, 25% fat calories, 60% carbohydrate calories, and 15% protein calories) increased venetoclax exposure by approximately 3.4-fold and administration with a high-fat meal (approximately 753 kilocalories, 55% fat calories, 28% carbohydrate calories, and 17% protein calories) increased venetoclax exposure by 5.1- to 5.3-fold compared with fasting conditions.

Distribution

Venetoclax is highly bound to human plasma protein with unbound fraction in plasma <0.01 across a concentration range of 1-30 micromolar (0.87-26 mcg/mL). The mean blood-to-plasma ratio was 0.57. The apparent volume of distribution (Vdss/F) of venetoclax ranged from 256-321 L in patients.

Elimination

The terminal elimination half-life of venetoclax was approximately 26 hours.

Metabolism

Venetoclax is predominantly metabolized by CYP3A in vitro. The major metabolite identified in plasma, M27, has an inhibitory activity against BCL-2 that is at least 58-fold lower than venetoclax in vitro and its AUC represented 80% of the parent AUC.

Excretion

After single oral dose of radiolabeled [^14C]-venetoclax 200 mg to healthy subjects, >99.9% of the dose was recovered in feces (21% as unchanged) and <0.1% in urine within 9 days.

Specific Populations

No clinically significant differences in the pharmacokinetics of venetoclax were observed based on age (19 to 93 years), sex, weight, mild to severe renal impairment (CLcr 15 to 89 mL/min, calculated by Cockcroft-Gault), or mild to moderate hepatic impairment (normal total bilirubin and aspartate transaminase (AST) > upper limit of normal (ULN) or total bilirubin 1 to 3 times ULN). The effect of end-stage renal disease (CLcr <15 mL/min) or dialysis on venetoclax pharmacokinetics is unknown.

Racial or Ethnic Groups

No clinically significant differences in the pharmacokinetics of venetoclax were observed in White, Black, and Asian patients enrolled in the United States. Of 771 patients with AML, Asian patients from Asian countries [China (5.6%), Japan (5.5%), South Korea (2.1%), and Taiwan (0.9%)] had 63% higher venetoclax exposure than non-Asian populations.

Patients with Hepatic Impairment

Following a single dose of VENCLEXTA 50 mg, venetoclax systemic exposure (AUC0-INF) was 2.7-fold higher in subjects with severe hepatic impairment (Child-Pugh C) compared to subjects with normal hepatic function [see Dosage and Administration (2.7) and Use in Specific Populations (8.7)]. No clinically relevant differences in venetoclax systemic exposure were observed between subjects with mild or moderate hepatic impairment and subjects with normal hepatic function.

Drug Interactions Studies

Clinical Studies

No clinically significant differences in venetoclax pharmacokinetics were observed when coadministered with azacitidine, azithromycin, cytarabine, decitabine, gastric acid reducing agents, obinutuzumab, or rituximab.

Ketoconazole

Concomitant use of ketoconazole (a strong CYP3A, P-gp, and BCRP inhibitor) 400 mg once daily for 7 days increased venetoclax Cmax by 130% and AUC0-INF by 540% [see Drug Interactions (7.1)].

Ritonavir

Concomitant use of ritonavir (a strong CYP3A, P-gp, and OATP1B1/B3 inhibitor) 50 mg once daily for 14 days increased venetoclax Cmax by 140% and AUC by 690% [see Drug Interactions (7.1)].

Posaconazole

Concomitant use of posaconazole (a strong CYP3A and P-gp inhibitor) 300 mg with VENCLEXTA 50 mg and 100 mg for 7 days resulted in 61% and 86% higher venetoclax Cmax, respectively, compared with VENCLEXTA 400 mg administered alone. The venetoclax AUC0-24h was 90% and 144% higher, respectively [see Drug Interactions (7.1)].

Rifampin

Concomitant use of a single dose of rifampin (an OATP1B1/1B3 and P-gp inhibitor) 600 mg increased venetoclax Cmax by 106% and AUC0-INF by 78%. Concomitant use of multiple doses of rifampin (as a strong CYP3A inducer) 600 mg once daily for 13 days decreased venetoclax Cmax by 42% and AUC0-INF by 71% [see Drug Interactions (7.1)].

Warfarin

Concomitant use of a single 400 mg dose of VENCLEXTA with 5 mg of warfarin resulted in 18% to 28% increase in Cmax and AUC0-INF of R-warfarin and S-warfarin [see Drug Interactions (7.2)].

Digoxin

Concomitant use of a single dose of VENCLEXTA 100 mg with digoxin (a P-gp substrate) 0.5 mg increased digoxin Cmax by 35% and AUC0-INF by 9% [see Drug Interactions (7.2)].

In Vitro Studies

Venetoclax is not an inhibitor or inducer of CYP1A2, CYP2B6, CYP2C19, CYP2D6, or CYP3A4. Venetoclax is a weak inhibitor of CYP2C8, CYP2C9, and UGT1A1.

Venetoclax is not an inhibitor of UGT1A4, UGT1A6, UGT1A9, or UGT2B7.

Venetoclax is an inhibitor and substrate of P-gp and BCRP and weak inhibitor of OATP1B1.

Venetoclax is not an inhibitor of OATP1B3, OCT1, OCT2, OAT1, OAT3, MATE1, or MATE2K.

13 NONCLINICAL TOXICOLOGY

13.1 Carcinogenesis, Mutagenesis, Impairment of Fertility

Neither venetoclax nor M27, a major human metabolite, were carcinogenic in a 6-month transgenic (Tg.rasH2) mouse study at oral doses up to 400 mg/kg/day of venetoclax, and at a single oral dose level of 250 mg/kg/day of M27.

Venetoclax was not mutagenic in an in vitro bacterial mutagenicity (Ames) assay, did not induce numerical or structural aberrations in an in vitro chromosome aberration assay using human peripheral blood lymphocytes, and was not clastogenic in an in vivo mouse bone marrow micronucleus assay at doses up to 835 mg/kg. The M27 metabolite was negative for genotoxic activity in in vitro Ames and chromosome aberration assays.

Fertility and early embryonic development studies were conducted in male and female mice. These studies evaluate mating, fertilization, and embryonic development through implantation. There were no effects of venetoclax on estrous cycles, mating, fertility, corpora lutea, uterine implants or live embryos per litter at dosages up to 600 mg/kg/day. However, a risk to human male fertility exists based on testicular toxicity (germ cell loss) observed in dogs at exposures as low as 0.5 times the human AUC exposure at a dose of 400 mg.

13.2 Animal Toxicology and/or Pharmacology

In dogs, venetoclax caused single-cell necrosis in various tissues, including the gallbladder, exocrine pancreas, and stomach with no evidence of disruption of tissue integrity or organ dysfunction; these findings were minimal to mild in magnitude. Following a 4-week dosing period and subsequent 4-week recovery period, minimal single-cell necrosis was still present in some tissues and reversibility has not been assessed following longer periods of dosing or recovery.

In addition, after approximately 3 months of daily dosing in dogs, venetoclax caused progressive white discoloration of the hair coat due to loss of melanin pigment.

14 CLINICAL STUDIES

14.1 Chronic Lymphocytic Leukemia/Small Lymphocytic Lymphoma

In Combination with Acalabrutinib

AMPLIFY (ACE-CL-311) was a randomized, multi-center, open-label study (NCT03836261) that evaluated the efficacy and safety of VENCLEXTA in combination with acalabrutinib (VEN+A). The study included patients previously untreated for CLL without del(17p) or TP53 mutation that were 18 years of age and older. Patients were randomized to receive:

- VENCLEXTA plus acalabrutinib (VEN+A): Acalabrutinib 100 mg was administered twice daily starting on Cycle 1 Day 1 for a total of 14 cycles or until disease progression or unacceptable toxicity. On Cycle 3 Day 1, patients started the VENCLEXTA 5-week dose-titration schedule, starting at 20 mg and increasing weekly to 50 mg, 100 mg, 200 mg and finally 400 mg once daily. VENCLEXTA was administered for a total of 12 cycles. Each cycle was 28 days.
- Investigator’s choice of chemoimmunotherapy (FCR/BR):
  - Fludarabine plus cyclophosphamide plus rituximab (FCR): Fludarabine (25 mg/m^2) and cyclophosphamide (250 mg/m^2) were administered on Days 1–3 up to a maximum of 6 cycles. Rituximab was administered at a dose of 375 mg/m^2 on Day 1 Cycle 1 and 500 mg/m^2 on Day 1 of Cycles 2 up to 6. Each cycle was 28 days.
  - Bendamustine plus rituximab (BR): Bendamustine 90 mg/m^2 was administered on Days 1 and 2 up to maximum of 6 cycles. Rituximab was administered at a dose of 375 mg/m^2 on Day 1 Cycle 1 and 500 mg/m^2 on Day 1 of Cycles 2 up to 6. Each cycle was 28 days.

- An additional investigational combination regimen [see Warnings and Precautions (5.3)].

Patients were stratified by age (>65 years or ≤65), IgVH mutational status (mutated versus unmutated), Rai stage (high risk [≥3] versus non-high risk) and geographic region (North America and Europe versus other). In the efficacy population described in Table 22, overall median age was 61 years (range: 26 to 86 years) and 62% were males; 89% were White, 3.8% Asian, 1.7% were Black or African American, 0.3% American Indian or Alaska Native, 0.3% Native Hawaiian or Other Pacific Islander, and 4.8% not reported; 86% were not Hispanic or Latino, 7% Hispanic or Latino, and 7% not reported. The ECOG performance was 0-1 in 90%, bulky disease with nodes ≥5 cm was seen in 41%, 45% had Rai stage III or IV disease, 17% had 11q deletion and 58% had unmutated IgVH.

The major efficacy outcome was based on progression-free survival (PFS) as assessed by an Independent Review Committee (IRC) of the VEN+A arm versus the Investigator’s choice (FCR/BR) arm. The median duration of follow-up for PFS was 42.6 months (range: 1 to 59 months) in the VEN+A arm. Efficacy results are presented in Table 22. The Kaplan-Meier curve for IRC-assessed PFS is shown in Figure 1.

Table 22. Efficacy Results in AMPLIFY – ITT Population
 | VENCLEXTA + acalabrutinib N = 291 |  | FCR/BRb N = 290
Progression-free survivala
Number of events, n (%) | 89 (31) |  | 95 (33)
Disease progression, n (%) | 77 (26) |  | 66 (23)
Death events (%) | 12 (4) |  | 29 (10)
Median, months (95% CI) | Not Reached (51.1, Not Reached) |  | 47.6 (43.3, Not Reached)
HRc (95% CI) | 0.65 (0.49, 0.87)
p-valued | 0.0038
Overall Response Rate (CR, CRi, nPR, PR) e
ORR n (%) | 270 (93) | 218 (75)
(95% CI) | (89, 95) | (70, 80)
CR | 26 (9) | 15 (5)
CRi, n (%) | 0 | 1 (0.3)
nPR, n (%) | 1 (0.3) | 1 (0.3)
PR n (%) | 243 (84) | 201 (69)
CR = complete response; CRi=complete response with incomplete blood count recovery; nPR=nodular partial response; PR=partial response
a Per IRC assessment.
b Approximately 50% of patients were treated with FCR and 50% were treated with BR per investigator's choice.
c Based on stratified Cox-Proportional-Hazards model.
d Based on stratified log-rank test. The pre-specified type I error rate (α) for this interim analysis is 0.0469 derived from a Lan-DeMets alpha spending function with O’Brien-Fleming boundary.
e Per iwCLL 2018 criteria

Figure 1. Kaplan-Meier Curve of IRC-Assessed Progression-free Survival in AMPLIFY

With a median follow-up of 41.0 months, a total of 60 death events were reported with 18 in the VEN+A arm and 42 in the FCR/BR arm.

In Combination with Obinutuzumab

CLL14 (BO25323) was a randomized (1:1), multicenter, open-label, actively controlled trial (NCT02242942) that evaluated the efficacy and safety of VENCLEXTA in combination with obinutuzumab (VEN+G) versus obinutuzumab in combination with chlorambucil (GClb) for patients with previously untreated CLL with coexisting medical conditions (total Cumulative Illness Rating Scale [CIRS] score >6 or CLcr <70 mL/min). The trial required hepatic transaminases and total bilirubin ≤2 times upper limit of normal and excluded patients with Richter’s transformation or any individual organ/system impairment score of 4 by CIRS except eye, ear, nose, and throat organ system.

All patients received obinutuzumab at 1000 mg on Days 1 (the first dose could be split as 100 mg and 900 mg on Days 1 and 2), 8 and 15 of Cycle 1, and on Day 1 of each subsequent cycle for a total of 6 cycles. Patients in the VEN+G arm began the VENCLEXTA 5-week ramp-up dosing schedule [see Dosage and Administration (2.2, 2.4)] on Day 22 of Cycle 1 and received VENCLEXTA 400 mg orally once daily from Cycle 3 Day 1 until the last day of Cycle 12. Patients randomized to the GClb arm received chlorambucil 0.5 mg/kg orally on Day 1 and Day 15 of Cycles 1 to 12. Each cycle was 28 days.

A total of 432 patients were randomized, 216 to each arm. Baseline demographic and disease characteristics were similar between the arms. The median age was 72 years (range: 41 to 89 years), 89% were White, 67% were male; 36% and 43% were Binet stage B and C, respectively, and 88% had Eastern Cooperative Oncology Group (ECOG) performance status <2. The median CIRS score was 8.0 (range: 0 to 28) and 58% of patients had CLcr <70 mL/min. A 17p deletion was detected in 8% of patients, TP53 mutations in 10%, 11q deletion in 19%, and unmutated IgVH in 57%.

Efficacy was based on progression-free survival (PFS) as assessed by an Independent Review Committee (IRC). The median duration of follow-up for PFS was 28 months (range: 0 to 36 months). Efficacy results for CLL14 are shown in Table 23. The Kaplan-Meier curve for PFS is shown in Figure 2.

Table 23. Efficacy Results in CLL14
Endpoint | VENCLEXTA + Obinutuzumab (N = 216) | Obinutuzumab + Chlorambucil (N = 216)
Progression-free survivala
Number of events, n (%) | 29 (13) | 79 (37)
Disease progression | 14 (6) | 71 (33)
Death | 15 (7) | 8 (4)
Median, months | Not Reached | Not Reached
HR (95% CI)b | 0.33 (0.22, 0.51)
p-valueb | <0.0001
Response ratec, n (%)
ORRd | 183 (85) | 154 (71)
95% CI | (79, 89) | (65, 77)
CR | 100 (46) | 47 (22)
CR+CRid | 107 (50) | 50 (23)
PR | 76 (35) | 104 (48)
CI = confidence interval; CR = complete remission; CRi = complete remission with incomplete marrow recovery; HR = hazard ratio; ORR = overall response rate (CR + CRi + PR); PR = partial remission.
aFrom randomization until earliest event of disease progression or death due to any cause. IRC-assessed; Kaplan-Meier estimate.
bHR estimate is based on Cox-proportional hazards model stratified by Binet Stage and geographic region; p-value based on log rank test stratified by the same factors.
cPer 2008 International Workshop for Chronic Lymphocytic Leukemia (IWCLL) guidelines.
dp-values based on Cochran-Mantel-Haenszel test; p=0.0007 for ORR; p<0.0001 for CR+CRi.

Figure 2. Kaplan-Meier Curve of IRC-Assessed Progression-free Survival in CLL14

At the time of analysis, median overall survival (OS) had not been reached, with fewer than 10% of patients experiencing an event. The median duration of follow-up for OS was 28 months.

Minimal residual disease (MRD) was evaluated using allele-specific oligonucleotide polymerase chain reaction (ASO-PCR). The definition of negative status was less than one CLL cell per 10^4 leukocytes. Rates of MRD negativity 3 months after the completion of treatment regardless of response and in patients who achieved CR are shown in Table 24. At this assessment, 134 patients in the VEN+G arm who were MRD negative in peripheral blood had matched bone marrow specimens; of these, 122 patients (91%) were MRD negative in both peripheral blood and bone marrow.

Table 24. Minimal Residual Disease Negativity Rates Three Months After the Completion of Treatment in CLL14
 | VENCLEXTA + Obinutuzumab | Obinutuzumab + Chlorambucil
MRD negativity rate (ITT population)
N | 216 | 216
Bone marrow, n (%) | 123 (57) | 37 (17)
95% CI | (50, 64) | (12, 23)
p-valuea | <0.0001
Peripheral blood, n (%) | 163 (76) | 76 (35)
95% CI | (69, 81) | (29, 42)
p-valuea | <0.0001
MRD negativity rate in patients with CR
N | 100 | 47
Bone marrow, n (%) | 69 (69) | 21 (45)
95% CI | (59, 78) | (30, 60)
p-valuea | 0.0048
Peripheral blood, n (%) | 87 (87) | 29 (62)
95% CI | (79, 93) | (46, 75)
p-valuea | 0.0005
CI = confidence interval; CR = complete remission.
ap-value based on Chi-square test.

Twelve months after the completion of treatment, MRD negativity rates in peripheral blood were 58% (126/216) in patients treated with VEN+G and 9% (20/216) in patients treated with GClb.

In Combination with Rituximab

MURANO was a randomized (1:1), multicenter, open-label trial (NCT02005471) that evaluated the efficacy and safety of VENCLEXTA in combination with rituximab (VEN+R) versus bendamustine in combination with rituximab (B+R) in patients with CLL who had received at least one line of prior therapy. Patients in the VEN+R arm completed the VENCLEXTA 5-week ramp-up dosing schedule [see Dosage and Administration (2.2, 2.4)] and received VENCLEXTA 400 mg orally once daily for 24 months from Cycle 1 Day 1 of rituximab in the absence of disease progression or unacceptable toxicity. Rituximab was initiated after the 5-week dose ramp-up at a dose of 375 mg/m^2 intravenously on Day 1 of Cycle 1 and 500 mg/m^2 intravenously on Day 1 of Cycles 2-6. Patients randomized to B+R received bendamustine 70 mg/m^2 intravenously on Days 1 and 2 for 6 cycles in combination with rituximab at the above described dose and schedule. Each cycle was 28 days.

A total of 389 patients were randomized: 194 to the VEN+R arm and 195 to the B+R arm. Baseline demographic and disease characteristics were similar between the VEN+R and B+R arms. The median age was 65 years (range: 22 to 85 years), 97% were White, 74% were male, and 99% had ECOG performance status <2. Median prior lines of therapy was 1 (range: 1 to 5); 59% had received 1 prior therapy, 26% had received 2 prior therapies, and 16% had received 3 or more prior therapies. Prior therapies included alkylating agents (94%), anti-CD20 antibodies (77%), B-cell receptor pathway inhibitors (2%), and prior purine analogs (81%, including fludarabine/cyclophosphamide/rituximab in 55%). A 17p deletion was detected in 24% of patients, TP53 mutations in 25%, 11q deletion in 32%, and unmutated IgVH in 63%.

Efficacy was based on PFS as assessed by an IRC. The median follow-up for PFS was 23.4 months (range: 0 to 37.4+ months). Efficacy results for MURANO are shown in Table 25. The Kaplan-Meier curve for PFS is shown in Figure 3.

Table 25. IRC-Assessed Efficacy Results in MURANO
Endpoint | VENCLEXTA + Rituximab (N = 194) | Bendamustine + Rituximab (N = 195)
Progression-free survivala
Number of events, n (%) | 35 (18) | 106 (54)
Disease progression, n | 26 | 91
Death events, n | 9 | 15
Median, months (95% CI) | Not Reached | 18.1 (15.8, 22.3)
HR (95% CI)b | 0.19 (0.13, 0.28)
p-valueb | <0.0001
Response ratec, n (%)
ORR | 179 (92) | 141 (72)
95% CI | (88, 96) | (65, 78)
CR+CRi | 16 (8) | 7 (4)
nPR | 3 (2) | 1 (1)
PR | 160 (82) | 133 (68)
CI = confidence interval; CR = complete remission; CRi = complete remission with incomplete marrow recovery; HR = hazard ratio; nPR = nodular partial remission; ORR = overall response rate (CR + CRi + nPR + PR); PR = partial remission.
aKaplan-Meier estimate.
bHR estimate is based on Cox-proportional hazards model stratified by 17p deletion, risk status, and geographic region; p-value based on log-rank test stratified by the same factors.
cPer 2008 International Workshop for Chronic Lymphocytic Leukemia (IWCLL) guidelines.

Figure 3. Kaplan-Meier Curve of IRC-Assessed Progression-free Survival in MURANO

At 3 months after the last dose of rituximab, the MRD negativity rate in peripheral blood in patients who achieved PR or better was 54% (104/194) in the VEN+R arm and 12% (23/195) in the B+R arm. The MRD-negative CR/CRi rate at this timepoint was 3% (6/194) in the VEN+R arm and 2% (3/195) in the B+R arm.

71-Month Follow-Up

With an overall follow-up of 71 months, the investigator-assessed median PFS was 53.6 months (95% CI: 48.4, 57.0) in the VEN+R arm and 17.0 months (95% CI: 15.5, 21.7) in the B+R arm. Median OS had not been reached in either arm. Death occurred in 16% (32/194) of patients in the VEN+R arm and 33% (64/195) of patients in the B+R arm (stratified HR 0.40; 95% CI [0.26, 0.62]). The Kaplan-Meier curve for OS is shown in Figure 4.

Figure 4. Kaplan-Meier Curve of Overall Survival in MURANO

Monotherapy

The efficacy of VENCLEXTA monotherapy in previously treated CLL or SLL is based on three single-arm trials.

M13-982

M13-982 (NCT01889186) was an open-label, multicenter trial that enrolled 106 patients with CLL with 17p deletion who had received at least one prior therapy. In the trial, 17p deletion was confirmed in peripheral blood specimens from patients using Vysis CLL FISH Probe Kit, which is FDA approved for selection of patients for VENCLEXTA treatment. Patients received VENCLEXTA 400 mg orally once daily following completion of the ramp-up dosing schedule [see Dosage and Administration (2.2, 2.4)].

Efficacy was based on overall response rate (ORR) as assessed by an IRC.

Table 26 summarizes the baseline demographic and disease characteristics of the trial population.

Table 26. Baseline Patient Characteristics in M13-982
Characteristic | N = 106
Age, years; median (range) | 67 (37-83)
White; % | 97
Male; % | 65
ECOG performance status; % 0 1 2 | 40 52 8
Tumor burden; % Absolute lymphocyte count ≥25 x 10^9/L One or more nodes ≥5 cm | 50 53
Number of prior therapies; median (range) | 2.5 (1-10)
Time since diagnosis, years; median (range)a | 6.6 (0.1-32.1)
ECOG = Eastern Cooperative Oncology Group.
aN=105.

The median time on treatment at the time of evaluation was 12.1 months (range: 0 to 21.5 months). Efficacy results are shown in Table 27.

Table 27. Efficacy Results per IRC for Patients with Previously Treated CLL with 17p Deletion in M13-982
Endpoint | VENCLEXTA N = 106
ORR, n (%)a (95% CI) | 85 (80) (71, 87)
CR + CRi, n (%) CR, n (%) CRi, n (%) | 8 (8) 6 (6) 2 (2)
nPR, n (%) | 3 (3)
PR, n (%) | 74 (70)
CI = confidence interval; CR = complete remission; CRi = complete remission with incomplete marrow recovery; IRC = independent review committee; nPR = nodular partial remission; ORR = overall response rate (CR + CRi + nPR + PR); PR = partial remission.
aPer 2008 IWCLL guidelines.

The median time to first response was 0.8 months (range: 0.1 to 8.1 months).

Based on a later data cutoff date and investigator-assessed efficacy, the duration of response (DOR) ranged from 2.9 to 32.8+ months. The median DOR has not been reached with median follow-up of 22 months.

Minimal residual disease was evaluated in peripheral blood and bone marrow for patients who achieved CR or CRi, following treatment with VENCLEXTA. Three percent (3/106) achieved MRD negativity in the peripheral blood and bone marrow (less than one CLL cell per 10^4 leukocytes).

M12-175

M12-175 (NCT01328626) was an open-label, multicenter trial that enrolled previously treated patients with CLL or SLL, including those with 17p deletion. Efficacy was evaluated in 67 patients (59 with CLL, 8 with SLL) who had received VENCLEXTA 400 mg orally once daily following completion of a ramp-up dosing schedule. Patients continued this dose until disease progression or unacceptable toxicity. The median duration of treatment at the time of evaluation was 22.1 months (range: 0.5 to 71.7 months).

The median age was 65 years (range: 42 to 84 years), 78% were male and 87% were White. The median number of prior treatments was 3 (range: 1 to 11). At baseline, 67% of patients had one or more nodes ≥5 cm, 30% of patients had ALC ≥25 x 10^9/L, 33% had documented unmutated IgVH, and 21% had documented 17p deletion.

Efficacy was based on 2008 IWCLL guidelines and assessed by an IRC. The ORR was 76% (95% CI: 64%, 86%), with a CR + CRi rate of 10% and PR rate of 66%. The median DOR was 36.2 months (range: 2.4 to 52.4 months).

M14-032

M14-032 (NCT02141282) was an open-label, multicenter trial that enrolled patients with CLL who had been previously treated with and progressed on or after ibrutinib or idelalisib. Patients received VENCLEXTA 400 mg orally once daily following completion of the ramp-up dosing schedule [see Dosage and Administration (2.2, 2.4)]. Patients continued this dose until disease progression or unacceptable toxicity. At the time of analysis, the median duration of treatment was 19.5 months (range: 0.1 to 39.5 months).

Of the 127 patients treated (91 with prior ibrutinib, 36 with prior idelalisib), the median age was 66 years (range: 28 to 85 years), 70% were male and 92% were White. The median number of prior treatments was 4 (range: 1 to 15). At baseline, 41% of patients had one or more nodes ≥5 cm, 31% had an ALC ≥25 x 10^9/L, 57% had documented unmutated IgVH, and 39% had documented 17p deletion.

Efficacy was based on 2008 IWCLL guidelines and was assessed by an IRC. The ORR was 70% (95% CI: 61%, 78%), with a CR + CRi rate of 5% and PR rate of 65%. The median DOR was not reached with a median follow-up time of 19.9 months (range: 2.9 to 36 months).

14.2 Acute Myeloid Leukemia

VENCLEXTA was studied in adult patients with newly diagnosed AML who were 75 years or older, or had comorbidities that precluded the use of intensive induction chemotherapy based on at least one of the following criteria: baseline ECOG performance status of 2-3, severe cardiac or pulmonary comorbidity, moderate hepatic impairment, CLcr <45 mL/min, or other comorbidity.

In Combination with Azacitidine or Decitabine

VIALE-A was a randomized (2:1), double-blind, placebo-controlled, multicenter trial (NCT02993523) that evaluated the efficacy and safety of VENCLEXTA in combination with azacitidine (VEN+AZA) versus placebo with azacitidine (PBO+AZA).

Patients received VENCLEXTA 400 mg orally once daily on Days 1-28 following completion of the ramp-up dosing schedule [see Dosage and Administration (2.3)] or placebo in combination with azacitidine 75 mg/m^2 either intravenously or subcutaneously on Days 1-7 of each 28-day cycle beginning on Cycle 1 Day 1. During the ramp-up, patients received TLS prophylaxis and were hospitalized for monitoring.

Once bone marrow assessment confirmed a remission, defined as less than 5% leukemia blasts with cytopenia following Cycle 1 treatment, VENCLEXTA or placebo was interrupted up to 14 days or until ANC ≥500/microliter and platelet count ≥50 × 10^3/microliter. For patients with resistant disease at the end of Cycle 1, a bone marrow assessment was performed after Cycle 2 or 3 and as clinically indicated. Azacitidine was resumed on the same day as VENCLEXTA or placebo following interruption. Azacitidine dose reduction was implemented in the clinical trial for management of hematologic toxicity [see Dosage and Administration (2.5)]. Patients continued treatment until disease progression or unacceptable toxicity.

A total of 431 patients were randomized: 286 to the VEN+AZA arm and 145 to the PBO+AZA arm. The baseline demographic and disease characteristic are shown in Table 28.

Table 28. Baseline Demographic and Disease Characteristics in Patients with AML in VIALE-A
Characteristic | VENCLEXTA + Azacitidine N = 286 | Placebo + Azacitidine N = 145
Age, years; median (range) | 76 (49, 91) | 76 (60, 90)
Race
White; % | 76 | 75
Black or African American; % | 1 | 1.4
Asian; % | 23 | 23
Males; % | 60 | 60
ECOG performance status; %
0-1 | 55 | 56
2 | 40 | 41
3 | 5.6 | 3.4
Bone marrow blast; %
<30% | 30 | 28
≥30% to <50% | 21 | 23
≥50% | 49 | 49
Disease history; %
De Novo AML | 75 | 76
Secondary AML | 25 | 24
Cytogenetic risk detecteda, %
Intermediate | 64 | 61
Poor | 36 | 39
Mutation analyses detected; n/Nb (%)
IDH1 or IDH2 | 61/245 (25) | 28/127 (22)
IDH1 | 23/245 (9.4) | 11/127 (8.7)
IDH2 | 40/245 (16) | 18/127 (14)
FLT3 | 29/206 (14) | 22/108 (20)
NPM1 | 27/163 (17) | 17/86 (20)
TP53 | 38/163 (23) | 14/86 (16)
aPer the 2016 National Comprehensive Cancer Network (NCCN) Guidelines.
bNumber of evaluable BMA specimens received at baseline.

Efficacy was based on overall survival (OS), measured from the date of randomization to death from any cause. The combination of VEN+AZA was superior in OS to PBO+AZA.

The Kaplan-Meier curve for OS is shown in Figure 5. The efficacy results of VIALE-A are shown in Table 29.

Figure 5. Kaplan-Meier Curve for Overall Survival in VIALE-A

Table 29. Efficacy Results in VIALE-A
Endpoint | VENCLEXTA + Azacitidine (N = 286) | Placebo + Azacitidine (N = 145)
Overall survival
Mediana, months (95% CI) | 14.7 (11.9, 18.7) | 9.6 (7.4, 12.7)
Hazard ratiob (95% CI) | 0.66 (0.52, 0.85)
p-valueb | <0.001
Response rate
CR, n (%) | 105 (37) | 26 (18)
(95% CI) | (31, 43) | (12, 25)
p-valuec | <0.001
Median DOCRa,d (months) | 18.0 | 13.4
95% CI | (15.3, -) | (8.7, 17.6)
CR+CRh, n (%) | 185 (65) | 33 (23)
(95% CI) | (59, 70) | (16, 30)
p-valuec | <0.001
Median DOCR+CRha,e (months) | 17.8 | 13.9
95% CI | (15.3, -) | (10.4, 15.7)
CI = confidence interval; CR = complete remission; CRh = complete remission with partial hematologic recovery; DOCR = duration of CR; HR = hazard ratio; - = not reached.
CR (complete remission) was defined as absolute neutrophil count >1,000/microliter, platelets >100,000/microliter, red blood cell transfusion independence, and bone marrow with <5% blasts. Absence of circulating blasts and blasts with Auer rods; absence of extramedullary disease.
CRh (complete remission with partial hematological recovery) was defined as <5% of blasts in the bone marrow, no evidence of disease, and partial recovery of peripheral blood counts (platelets >50,000/microliter and ANC >500/microliter).
aKaplan-Meier estimate.
bHazard ratio estimate (VEN+AZA vs. PBO+AZA) is based on Cox-proportional hazards model stratified by cytogenetics (intermediate risk, poor risk) and age (18 to <75, ≥75 years) as assigned at randomization; p-value based on log-rank test stratified by the same factors.
cp-value is from Cochran-Mantel-Haenszel test stratified by age and cytogenetics risk.
dDuration of CR is defined as the number of days from the date of first response of CR to the date of earliest evidence of confirmed morphologic relapse, confirmed progressive disease or death due to disease progression.
eDuration of CR+CRh is defined as the number of days from the date of first response of CR+CRh (the first of either CR or CRh) to the date of earliest evidence of confirmed morphologic relapse, confirmed progressive disease, or death due to disease progression.

Among the patients treated with VEN+AZA, 155 were dependent on red blood cell (RBC) and/or platelets transfusions at baseline; of these patients, 49% (76/155) became independent of RBC and platelet transfusions during any consecutive ≥56-day post-baseline period. Of the patients treated with VEN+AZA, 131 were independent of both RBC and platelet transfusions at baseline, 69% (90/131) remained transfusion independent during any consecutive ≥56-day post-baseline period. Among the patients treated with PBO+AZA, 81 were dependent on RBC and/or platelets transfusions at baseline; of these patients, 27% (22/81) patients became independent of RBC and platelet transfusions during any consecutive ≥56-day post-baseline period. Of the patients treated with PBO+AZA, 64 were independent of both RBC and platelet transfusions at baseline, 42% (27/64) remained transfusion independent during any consecutive ≥56-day post-baseline period.

The median time to first response of CR or CRh was 1.0 months (range: 0.6 to 14.3 months) with VEN+AZA treatment.

M14-358

M14-358 (NCT02203773) was a non-randomized, open-label trial that evaluated the efficacy of VENCLEXTA in combination with azacitidine (N=84) or decitabine (N=31) in patients with newly diagnosed AML. Of those patients, 67 who received azacitidine combination and 13 who received decitabine combination were 75 years or older, or had comorbidities that precluded the use of intensive induction chemotherapy.

Patients received VENCLEXTA 400 mg orally once daily following completion of the ramp-up dosing schedule [see Dosage and Administration (2.3)] in combination with azacitidine (75 mg/m^2 either intravenously or subcutaneously on Days 1-7 of each 28-day cycle beginning on Cycle 1 Day 1) or decitabine (20 mg/m^2 intravenously on Days 1-5 of each 28-day cycle beginning on Cycle 1 Day 1). During the ramp-up phase, patients received TLS prophylaxis and were hospitalized for monitoring. Patients continued treatment until disease progression or unacceptable toxicity. Once bone marrow assessment confirmed a remission, defined as less than 5% leukemia blasts, with cytopenia following Cycle 1 treatment, VENCLEXTA was interrupted up to 14 days or until ANC ≥500/microliter and platelet count ≥50 × 10^3/microliter. Azacitidine dose reduction was implemented in the clinical trial for management of hematologic toxicity [see Dosage and Administration (2.5)]. Dose reductions for decitabine were not implemented in the clinical trial. Baseline demographic and disease characteristic are shown in Table 30.

Table 30. Baseline Patient Characteristics for Patients with AML Treated with VENCLEXTA in Combination with Azacitidine or Decitabine
Characteristic | VENCLEXTA + Azacitidine N = 67 | VENCLEXTA + Decitabine N = 13
Age, years; median (range) | 76 (61-90) | 75 (68-86)
Race; %
White | 87 | 77
Black or African American | 4.5 | 0
Asian | 1.5 | 0
Native Hawaiian or Pacific Islander | 1.5 | 15
American Indian/Alaskan Native | 0 | 7.7
Unreported other | 6 | 0
Male; % | 60 | 38
ECOG performance status; % 0-1 2 3 | 64 33 3 | 92 7.7 0
Disease history; % De Novo AML Secondary AML | 73 27 | 85 15
Mutation analyses detecteda; %
TP53 | 15 | 31
IDH1 or IDH2 | 27 | 0
FLT3 | 16 | 23
NPM1 | 19 | 15
Cytogenetic risk detectedb,c; %
Intermediate | 64 | 38
Poor | 34 | 62
Baseline comorbiditiesd; %
Severe cardiac disease | 4.5 | 7.7
Severe pulmonary disease | 1.5 | 0
Moderate hepatic impairment | 9 | 0
Creatinine clearance <45 mL/min | 13 | 7.7
ECOG = Eastern Cooperative Oncology Group.
aIncludes 6 patients with insufficient sample for analysis in the azacitidine group and 4 in the decitabine group.
bAs defined by the National Comprehensive Cancer Network (NCCN) risk categorization v2014.
cNo mitosis in 1 patient in azacitidine group (excluded favorable risk by Fluorescence in situ Hybridization [FISH] analysis).
dPatients may have had more than one comorbidity.

The efficacy results are shown in Table 31.

Table 31. Efficacy Results for Patients with Newly Diagnosed AML Treated with VENCLEXTA in Combination with Azacitidine or Decitabine
Efficacy Outcomes | VENCLEXTA + Azacitidine N = 67 | VENCLEXTA + Decitabine N = 13
CR, n (%) | 29 (43) | 7 (54)
(95% CI) | (31, 56) | (25, 81)
CRh, n (%) | 12 (18) | 1 (7.7)
(95% CI) | (9.6, 29) | (0.2, 36)
CI = confidence interval; CR = complete remission; CRh = complete remission with partial hematological recovery.

The median follow-up was 15.9 months (range: 0.4 to 40.3 months) for VENCLEXTA in combination with azacitidine. The median duration of CR was 23.8 months (95% CI: 15.4, -), and the median duration of CR+CRh was 26.5 months (95% CI: 17.4, -).

The median follow-up was 11.0 months (range: 0.7 to 38.8 months) for VENCLEXTA in combination with decitabine. The median duration of CR was 12.7 months (95% CI: 1.4, -) and median duration of CR+CRh was 12.7 months (95% CI: 1.4, 20.0).

Duration of CR is defined as time from the first documentation of CR to the first date of relapse, clinical disease progression or death due to disease progression, whichever occurred earliest. Duration of CR+CRh is defined as time from the first documentation of either CR or CRh to the first date of relapse, clinical disease progression or death due to disease progression, whichever occurred earliest.

Median time to first CR or CRh for patients treated with VENCLEXTA in combination with azacitidine was 1.0 month (range: 0.7 to 8.9 months).

Median time to first CR or CRh for patients treated with VENCLEXTA in combination with decitabine was 1.9 months (range: 0.8 to 4.2 months).

Of patients treated with VENCLEXTA in combination with azacitidine, 12% (8/67) subsequently received stem cell transplant.

The trial enrolled 35 additional patients (age range: 65 to 74 years) who did not have known comorbidities that precluded the use of intensive induction chemotherapy and were treated with VENCLEXTA in combination with azacitidine (N=17) or decitabine (N=18).

For the 17 patients treated with VENCLEXTA in combination with azacitidine, the CR rate was 35% (95% CI: 14%, 62%). The CRh rate was 41% (95% CI: 18%, 67%). Nine (53%) patients subsequently received stem cell transplant.

For the 18 patients treated with VENCLEXTA in combination with decitabine, the CR rate was 56% (95% CI: 31%, 79%). The CRh rate was 22% (95% CI: 6.4%, 48%). Four (22%) patients subsequently received stem cell transplant.

In Combination with Low-Dose Cytarabine

VIALE-C was a randomized (2:1), double-blind, placebo-controlled, multicenter trial (NCT03069352) that evaluated the efficacy and safety of VENCLEXTA in combination with low-dose cytarabine (VEN+LDAC) versus placebo with low-dose cytarabine (PBO+LDAC).

Patients received VENCLEXTA 600 mg orally once daily on Days 1-28 following completion of the ramp-up dosing schedule [see Dosage and Administration (2.3)] or placebo in combination with cytarabine 20 mg/m^2 subcutaneously once daily on Days 1-10 of each 28-day cycle beginning on Cycle 1 Day 1. During the ramp-up phase, patients received TLS prophylaxis and were hospitalized for monitoring.

Once bone marrow assessment confirmed a remission, defined as less than 5% leukemia blasts with cytopenia following Cycle 1 treatment, VENCLEXTA or placebo was interrupted up to 14 days or until ANC ≥500/microliter and platelet count ≥50 × 10^3/microliter. For patients with resistant disease at the end of Cycle 1, a bone marrow assessment was performed after Cycle 2 or 3 and as clinically indicated. LDAC was resumed on the same day as VENCLEXTA or placebo following interruption. Patients continued to receive treatment until disease progression or unacceptable toxicity. Baseline demographic and disease characteristic are shown in Table 32.

Table 32. Baseline Demographic and Disease Characteristics in Patients with AML in VIALE-C
Characteristic | VENCLEXTA + Low-Dose Cytarabine N = 143 | Placebo + Low-Dose Cytarabine N = 68
Age, years; median (range) | 76 (36, 93) | 76 (41, 88)
Race; %
White | 71 | 69
Black or African American | 1.4 | 1.5
Asian | 27 | 29
Male; % | 55 | 57
ECOG performance status; % 0-1 2 3 | 52 44 4.2 | 50 37 13
Disease history; % De Novo AML Secondary AML | 59 41 | 66 34
Mutation analyses detected; n/Na (%)
TP53 | 22/112 (20) | 9/52 (17)
IDH1 or IDH2 | 21/112 (19) | 12/52 (23)
FLT3 | 20/112 (18) | 9/52 (17)
NPM1 | 18/112 (16) | 7/52 (13)
Cytogenetic risk detectedb; %
Favorable | <1 | 4
Intermediate | 63 | 63
Poor | 33 | 29
aNumber of evaluable BMA specimens received at baseline.
bPer the 2016 National Comprehensive Cancer Network (NCCN) Guidelines.

Efficacy was based on the rate of CR and duration of CR with supportive evidence of rate of CR+CRh, duration of CR+CRh, and the rate of conversion from transfusion dependence to transfusion independence. The CR rate in the VEN+LDAC arm was 27% (95% CI: 20%, 35%) with a median duration of CR of 11.1 months (95% CI: 6.1, -), and the CR rate in the PBO+LDAC arm was 7.4% (95% CI: 2.4%, 16%) with a median duration of CR of 8.3 months (95% CI: 3.1, -). The CR+CRh rate in the VEN+LDAC arm was 47% (95% CI: 39%, 55%) and in the PBO+LDAC arm was 15% (95% CI: 7.3%, 25%) with a median duration of CR+CRh of 11.1 months with VEN+LDAC treatment and 6.2 months with PBO+LDAC treatment. The median time to first response of CR or CRh was 1.0 month (range: 0.7 to 5.8 months) with VEN+LDAC treatment.

Among the patients treated with VEN+LDAC, 111 were dependent on RBC and/or platelets transfusions at baseline; of these patients, 33% (37/111) patients became independent of RBC and platelet transfusions during any consecutive ≥56-day post-baseline period. Of the patients treated with VEN+LDAC, 32 were independent of both RBC and platelet transfusions at baseline, 50% (16/32) remained transfusion independent during any consecutive ≥56-day post-baseline period.

Among the patients treated with PBO+LDAC, 55 were dependent on RBC and/or platelets transfusions at baseline; of these patients, 13% (7/55) patients became independent of RBC and platelet transfusions during any consecutive ≥56-day post-baseline period. Of the patients treated with PBO+LDAC, 13 were independent of both RBC and platelet transfusions at baseline, 31% (4/13) remained transfusion independent during any consecutive ≥56-day post-baseline period.

VEN+LDAC did not significantly improve OS versus PBO+LDAC. The hazard ratio (HR) for OS was 0.75 (95% CI: 0.52, 1.07); p-value 0.114. The median OS for VEN+LDAC arm was 7.2 months (95% CI: 5.6, 10.1) and for PBO+LDAC arm was 4.1 months (95% CI: 3.1, 8.8).

M14-387

M14-387 (NCT02287233) was a non-randomized, open-label trial that evaluated the efficacy of VEN+LDAC (N=82) in patients with newly diagnosed AML, including patients with previous exposure to a hypomethylating agent for an antecedent hematologic disorder. Of those patients, 61 were 75 years or older, or had comorbidities that precluded the use of intensive induction chemotherapy.

Patients received VENCLEXTA 600 mg orally once daily on Days 1-28 following completion of the ramp-up phase [see Dosage and Administration (2.3)] in combination with cytarabine 20 mg/m^2 subcutaneously once daily on Days 1-10 of each 28-day cycle beginning on Cycle 1 Day 1. During the ramp-up, patients received TLS prophylaxis and were hospitalized for monitoring. Once bone marrow assessment confirmed a remission, defined as less than 5% leukemia blasts with cytopenia following Cycle 1 treatment, VENCLEXTA was interrupted up to 14 days or until ANC ≥500/microliter and platelet count ≥50 × 10^3/microliter. Patients continued treatment until disease progression or unacceptable toxicity. Baseline demographic and disease characteristic are shown in Table 33.

Table 33. Baseline Patient Characteristics for Patients with AML Treated with VENCLEXTA in Combination with Low-Dose Cytarabine
Characteristic | VENCLEXTA in Combination with Low-Dose Cytarabine N = 61
Age, years; median (range) | 76 (63-90)
Race; %
White | 92
Black or African American | 1.6
Asian | 1.6
Unreported | 4.9
Male; % | 74
ECOG performance status; % 0-1 2 3 | 66 33 1.6
Disease history; % De Novo AML Secondary AML | 54 46
Mutation analyses detecteda; %
TP53 | 8.2
IDH1 or IDH2 | 23
FLT3 | 21
NPM1 | 9.8
Cytogenetic risk detectedb; %
Intermediate | 59
Poor | 34
No mitoses | 6.6
Baseline comorbiditiesc; %
Severe cardiac disease | 9.8
Moderate hepatic impairment | 4.9
Creatinine clearance ≥30 or <45 mL/min | 3.3
aIncludes 7 patients with insufficient sample for analysis.
bAs defined by the National Comprehensive Cancer Network (NCCN) risk categorization v2014.
cPatients may have had more than one comorbidity.

The median follow-up was 7.3 months (range: 0.3 to 54.0 months). The CR rate was 21% (95% CI: 12, 34) and CRh rate was 21% (95% CI: 12, 34).

The median duration of CR was 22.9 months (95% CI: 5.1, -) and the median duration of CR+CRh was 14.3 months (95% CI: 6.1, 31.2).

Median time to first CR or CRh for patients treated with VEN+LDAC was 1.0 month (range: 0.8 to 9.4 months).

The trial enrolled 21 additional patients (age range: 67 to 74 years) who did not have known comorbidities that precluded the use of intensive induction chemotherapy and were treated with VEN+LDAC. The CR rate was 33% (95% CI: 15%, 57%). The CRh rate was 24% (95% CI: 8.2%, 47%). One patient (4.8%) subsequently received stem cell transplant.

16 HOW SUPPLIED/STORAGE AND HANDLING

VENCLEXTA is dispensed as follows:

Packaging Presentation | Number of Tablets | National Drug Code (NDC)
CLL/SLL Starting Pack | Each pack contains four weekly wallet blister packs:; - Week 1 (14 x 10 mg tablets) - Week 2 (7 x 50 mg tablets) - Week 3 (7 x 100 mg tablets) - Week 4 (14 x 100 mg tablets) | 0074-0579-28
Wallet containing 10 mg tablets | 14 x 10 mg tablets | 0074-0561-14
Wallet containing 50 mg tablets | 7 x 50 mg tablets | 0074-0566-07
Unit dose blister containing 10 mg tablets | 2 x 10 mg tablets | 0074-0561-11
Unit dose blister containing 50 mg tablet | 1 x 50 mg tablet | 0074-0566-11
Unit dose blister containing 100 mg tablet | 1 x 100 mg tablet | 0074-0576-11
Bottle containing 100 mg tablets | 28 x 100 mg tablets | 0074-0576-30
Bottle containing 100 mg tablets | 120 x 100 mg tablets | 0074-0576-22

VENCLEXTA 10 mg film-coated tablets are round, biconvex shaped, pale yellow debossed with “V” on one side and “10” on the other side.

VENCLEXTA 50 mg film-coated tablets are oblong, biconvex shaped, beige debossed with “V” on one side and “50” on the other side.

VENCLEXTA 100 mg film-coated tablets are oblong, biconvex shaped, pale yellow debossed with “V” on one side and “100” on the other side.

Store in original container at or below 86°F (30°C). Dispense to patient in original container to protect from moisture.

17 PATIENT COUNSELING INFORMATION

Advise the patient to read the FDA-approved patient labeling (Medication Guide).

Tumor Lysis Syndrome

Advise patients of the potential risk of TLS, particularly at treatment initiation, during the ramp-up phase, and with resumption after an interruption and to immediately report any signs and symptoms associated with this event (fever, chills, nausea, vomiting, confusion, shortness of breath, seizure, irregular heartbeat, dark or cloudy urine, unusual tiredness, muscle or bone pain, and/or joint discomfort) to their health care provider (HCP) for evaluation [see Warnings and Precautions (5.1)].

Advise patients to be adequately hydrated every day when taking VENCLEXTA to reduce the risk of TLS. The recommended volume is 6 to 8 glasses (approximately 56 ounces total) of water each day. Patients should drink water starting 2 days before and on the day of the first dose, and every time the dose is increased [see Dosage and Administration (2.4)].

Advise patients of the importance of keeping scheduled appointments for blood work or other laboratory tests [see Dosage and Administration (2.4)].

Advise patients that it may be necessary to take VENCLEXTA in the hospital or medical office setting to allow monitoring for TLS.

Neutropenia

Advise patients to contact their HCP immediately if they develop a fever or any signs of infection. Advise patients of the need for periodic monitoring of blood counts [see Warnings and Precautions (5.2)].

Infections

Advise patients to contact their HCP immediately if they develop a fever or any signs of infection [see Warnings and Precautions (5.3)].

Drug Interactions

Advise patients to avoid consuming grapefruit products, Seville oranges, or starfruit during treatment with VENCLEXTA. Advise patients that VENCLEXTA may interact with some drugs; therefore, advise patients to inform their health care provider of the use of any prescription medication, over-the-counter drugs, vitamins and herbal products [see Contraindications (4) and Drug Interactions (7.1)].

Immunizations

Advise patients to avoid vaccination with live vaccines because they may not be safe or effective during treatment with VENCLEXTA [see Warnings and Precautions (5.4)].

Embryo-Fetal Toxicity

Advise pregnant women of the potential risk to the fetus. Advise females or reproductive potential to inform their healthcare provider of a known or suspected pregnancy [see Warnings and Precautions (5.5) and Use in Specific Populations (8.1)].

Advise female patients of reproductive potential to use effective contraception during therapy and for 30 days after the last dose [see Use in Specific Populations (8.3)].

Lactation

Advise women not to breastfeed during treatment with VENCLEXTA and for 1 week after the last dose [see Use in Specific Populations (8.2)].

Infertility

Advise males of reproductive potential that VENCLEXTA may impair fertility [see Use in Specific Populations (8.3)].

Administration

Advise patients to keep VENCLEXTA in original packaging or container.

Advise patients to take VENCLEXTA exactly as prescribed and not to change their dose or to stop taking VENCLEXTA unless they are told to do so by their HCP. Advise patients to take VENCLEXTA orally once daily, at approximately the same time each day, according to their HCP's instructions and that the tablets should be swallowed whole with a meal and water without being chewed, crushed, or broken [see Dosage and Administration (2.8)].

Advise patients that if a dose of VENCLEXTA is missed by less than 8 hours, to take the missed dose right away and take the next dose as usual. If a dose of VENCLEXTA is missed by more than 8 hours, advise patients to wait and take the next dose at the usual time [see Dosage and Administration (2.8)].

Advise patients not to take any additional dose that day if they vomit after taking VENCLEXTA, and to take the next dose at the usual time the following day.

Manufactured and Marketed by:
AbbVie Inc.
North Chicago, IL 60064

and

Marketed by:
Genentech USA, Inc.
A Member of the Roche Group
South San Francisco, CA 94080-4990

© 2026 AbbVie. All rights reserved.
Venclexta and its design are trademarks of AbbVie Inc.
© 2026 Genentech, Inc. All rights reserved.
20098663 R1

MEDICATION GUIDE
VENCLEXTA® (ven-KLEKS-tuh)
(venetoclax tablets)

What is the most important information I should know about VENCLEXTA?
VENCLEXTA can cause serious side effects, including:

- Tumor lysis syndrome (TLS). TLS is caused by the fast breakdown of cancer cells. TLS can cause kidney failure, the need for dialysis treatment, and may lead to death. Your healthcare provider will do tests to check your risk of getting TLS before you start taking VENCLEXTA. You will receive other medicines before starting and during treatment with VENCLEXTA to help reduce your risk of TLS. You may also need to receive intravenous (IV) fluids into your vein. Your healthcare provider will do blood tests to check for TLS when you first start and during treatment with VENCLEXTA. It is important to keep your appointments for blood tests. Tell your healthcare provider right away if you get any symptoms of TLS during treatment with VENCLEXTA, including:

○ fever
○ chills
○ nausea
○ vomiting
○ confusion
○ shortness of breath

○ seizures
○ irregular heartbeat
○ dark or cloudy urine
○ unusual tiredness
○ muscle or joint pain

Drink plenty of water during treatment with VENCLEXTA to help reduce your risk of getting TLS.
Drink 6 to 8 glasses (about 56 ounces total) of water each day, starting 2 days before your first dose, on the day of your first dose of VENCLEXTA, and each time your dose is increased.
Your healthcare provider may delay, decrease your dose, or stop treatment with VENCLEXTA if you get symptoms of TLS. When restarting VENCLEXTA after stopping for 1 week or longer, your healthcare provider may again check for your risk of TLS and change your dose.
See "What are the possible side effects of VENCLEXTA?" for more information about side effects.

What is VENCLEXTA?
VENCLEXTA is a prescription medicine used:

- to treat adults with chronic lymphocytic leukemia (CLL) or small lymphocytic lymphoma (SLL).
- in combination with azacitidine, or decitabine, or low-dose cytarabine to treat adults with newly diagnosed acute myeloid leukemia (AML) who:
  ○ are 75 years of age or older, or
  ○ have other medical conditions that prevent the use of standard chemotherapy.

It is not known if VENCLEXTA is safe and effective in children.

Who should not take VENCLEXTA?
Patients taking certain medicines during the beginning of VENCLEXTA (when the dose is being slowly increased) are at increased risk of TLS.

- Tell your healthcare provider about all the medicines you take, including prescription and over-the-counter medicines, vitamins, and herbal supplements. VENCLEXTA and other medicines may affect each other causing serious side effects.
- Do not start new medicines during treatment with VENCLEXTA without first talking with your healthcare provider.

Before taking VENCLEXTA, tell your healthcare provider about all of your medical conditions, including if you:

- have kidney problems
- have liver problems
- have problems with your body salts or electrolytes, such as potassium, phosphorus, or calcium
- have a history of high uric acid levels in your blood or gout
- are scheduled to receive a vaccine. You should not receive a “live vaccine” before, during, or after treatment with VENCLEXTA, until your healthcare provider tells you it is okay. If you are not sure about the type of immunization or vaccine, ask your healthcare provider. These vaccines may not be safe or may not work as well during treatment with VENCLEXTA.
- are pregnant or plan to become pregnant. VENCLEXTA may harm your unborn baby.
  Females who are able to become pregnant:
  - Your healthcare provider should do a pregnancy test before you start treatment with VENCLEXTA.
  - Use effective birth control during treatment and for 30 days after the last dose of VENCLEXTA.
  - If you become pregnant or think you are pregnant, tell your healthcare provider right away.
- are breastfeeding or plan to breastfeed. It is not known if VENCLEXTA passes into your breast milk. Do not breastfeed during treatment and for 1 week after the last dose of VENCLEXTA.

Tell your healthcare provider about all the medicines you take, including prescription and over-the-counter medicines, vitamins, and herbal supplements. VENCLEXTA and other medicines may affect each other causing serious side effects. See “Who should not take VENCLEXTA?”

How should I take VENCLEXTA?

- Take VENCLEXTA exactly as your healthcare provider tells you to take it. Do not change your dose of VENCLEXTA or stop taking VENCLEXTA unless your healthcare provider tells you to.
- When you first take VENCLEXTA:
  ○ You may need to take VENCLEXTA at a hospital or clinic to be monitored for TLS.
  ○ If you take VENCLEXTA for CLL or SLL, your healthcare provider will start VENCLEXTA at a low dose. Your dose will be slowly increased weekly over 5 weeks up to the full dose. Read the Quick Start Guide that comes with VENCLEXTA before your first dose.
  ○ If you take VENCLEXTA for AML, your healthcare provider will start VENCLEXTA at a low dose. Your dose will be slowly increased daily over 3 or 4 days up to the full dose. Follow your healthcare provider’s instructions carefully while increasing to the full dose.
- Follow the instructions about drinking water described in the section of this Medication Guide about TLS called “What is the most important information I should know about VENCLEXTA?” and also in the Quick Start Guide.
- Take VENCLEXTA 1 time a day with a meal and water at about the same time each day.
- Swallow VENCLEXTA tablets whole. Do not chew, crush, or break the tablets.
- Tell your healthcare provider if you have trouble swallowing 100 mg VENCLEXTA tablets. Your healthcare provider may prescribe your dose in smaller sized tablets.
- If you miss a dose of VENCLEXTA and it has been less than 8 hours, take your dose as soon as possible. If you miss a dose of VENCLEXTA and it has been more than 8 hours, skip the missed dose and take the next dose at your usual time.
- If you vomit after taking VENCLEXTA, do not take an extra dose. Take the next dose at your usual time the next day.

What should I avoid while taking VENCLEXTA?
You should not drink grapefruit juice, eat grapefruit, Seville oranges (often used in marmalades), or starfruit during treatment with VENCLEXTA. These products may increase the amount of VENCLEXTA in your blood.

What are the possible side effects of VENCLEXTA?
VENCLEXTA can cause serious side effects, including:

- See "What is the most important information I should know about VENCLEXTA?"
- Low white blood cell count (neutropenia). Your healthcare provider will do blood tests to check your blood count during treatment with VENCLEXTA and may pause dosing of VENCLEXTA or give you medicines to help treat your neutropenia if it is severe.
- Infections. Death and serious infections such as pneumonia and blood infection (sepsis) have happened during treatment with VENCLEXTA. Your healthcare provider will closely monitor and treat you right away if you get a fever or any signs of infection during treatment with VENCLEXTA.

Tell your healthcare provider right away if you get a fever or any signs of an infection during treatment with VENCLEXTA.
The most common side effects of VENCLEXTA when used in combination with obinutuzumab, or rituximab, or alone in people with CLL or SLL include:

- low white blood cell count
- low platelet count
- low red blood cell count
- diarrhea
- nausea

- upper respiratory tract infection
- cough
- muscle and joint pain
- tiredness
- swelling of your arms, legs, hands, and feet

The most common side effects of VENCLEXTA when used in combination with acalabrutinib in people with CLL or SLL include:

- low white blood cell count
- headache
- diarrhea

- muscle and bone pain
- COVID-19

The most common side effects of VENCLEXTA in combination with azacitidine, or decitabine, or low-dose cytarabine in people with AML include:

- nausea
- diarrhea
- low platelet count
- constipation
- low white blood cell count
- fever with low white blood cell count
- tiredness
- vomiting
- swelling of arms, legs, hands, or feet
- fever
- infection in lungs

- shortness of breath
- bleeding
- low red blood cell count
- rash
- stomach (abdominal) pain
- infection in your blood
- muscle and joint pain
- dizziness
- cough
- sore throat
- low blood pressure

Your healthcare provider may temporarily stop VENCLEXTA treatment, decrease your dose, or completely stop treatment if you get severe side effects.
VENCLEXTA may cause fertility problems in males. This may affect your ability to father a child. Talk to your healthcare provider if you have concerns about fertility.
These are not all the possible side effects of VENCLEXTA. Call your doctor for medical advice about side effects. You may report side effects to FDA at 1-800-FDA-1088.

How should I store VENCLEXTA?

- Store VENCLEXTA at or below 86°F (30°C).
- Keep VENCLEXTA in its original packaging or container to protect from moisture.

Keep VENCLEXTA and all medicines out of reach of children.

General information about the safe and effective use of VENCLEXTA.
Medicines are sometimes prescribed for purposes other than those listed in a Medication Guide. Do not use VENCLEXTA for a condition for which it was not prescribed. Do not give VENCLEXTA to other people, even if they have the same symptoms that you have. It may harm them. You can ask your healthcare provider or pharmacist for information about VENCLEXTA that is written for health professionals.

What are the ingredients in VENCLEXTA?
Active ingredient: venetoclax
Inactive ingredients: copovidone, colloidal silicon dioxide, polysorbate 80, sodium stearyl fumarate, and calcium phosphate dibasic.
The 10 mg and 100 mg coated tablets also include: iron oxide yellow, polyvinyl alcohol, polyethylene glycol, talc, and titanium dioxide. The 50 mg coated tablets also include: iron oxide yellow, iron oxide red, iron oxide black, polyvinyl alcohol, talc, polyethylene glycol, and titanium dioxide.

Manufactured and Marketed by:
AbbVie Inc.
North Chicago, IL 60064
© 2026 AbbVie. All rights reserved.
Venclexta and its design are trademarks of AbbVie Inc.
20098663 R1

Marketed by:
Genentech USA, Inc.
A Member of the Roche Group
South San Francisco, CA 94080-4990
© 2026 Genentech, Inc. All rights reserved.

For more information go to www.venclexta.com or call 1-800-633-9110

This Medication Guide has been approved by the U.S. Food and Drug Administration.

Revised: 2/2026

PACKAGE LABEL

NDC 0074-0579-28

CLL/SLL Starting Pack

VENCLEXTA®

(venetoclax tablets)

10 mg, 50 mg, and 100 mg

Starting Pack

! WARNING

Contact your doctor when you receive this medication.

It may be necessary to take your first dose in the presence of your doctor to prevent a potential serious side effect.

DISPENSER: Each time VENCLEXTA is dispensed give the patient the enclosed Medication Guide.

abbvie

Rx only

Genentech

PACKAGE LABEL

NDC 0074-0561-14

Rx only

VENCLEXTA®

(venetoclax tablets)

10 mg per tablet

14 Tablets

Dispense the accompanying Medication Guide to each patient.

abbvie

Genentech

PACKAGE LABEL

NDC 0074-0566-11

Rx only

VENCLEXTA®

(venetoclax tablets)

50 mg per tablet

1 Tablet

Dispense the accompanying Medication Guide to each patient.

abbvie

Genentech

PACKAGE LABEL

NDC 0074-0576-22

Rx only

VENCLEXTA®

(venetoclax tablets)

100 mg

Attention: Dispense and store Venclexta in original container to protect from moisture.

120 Tablets

Dispense the accompanying Medication Guide to each patient.

abbvie

Genetech